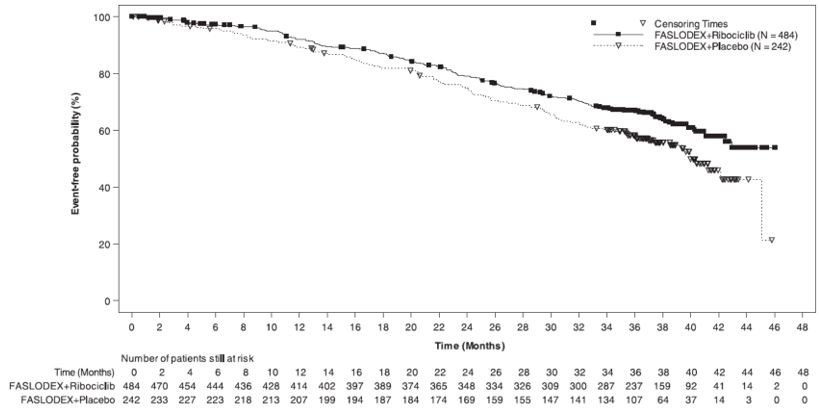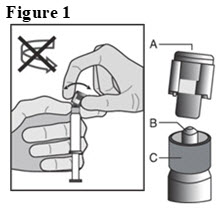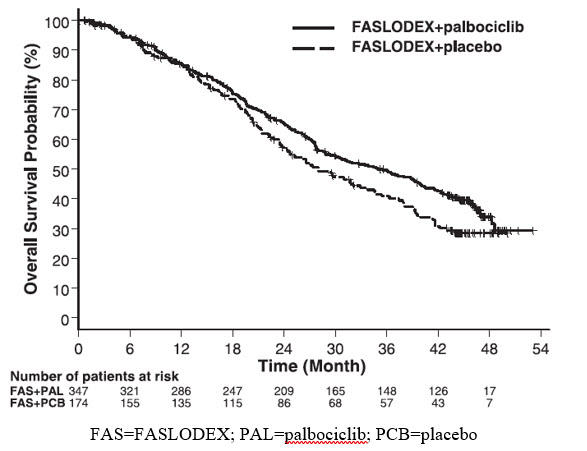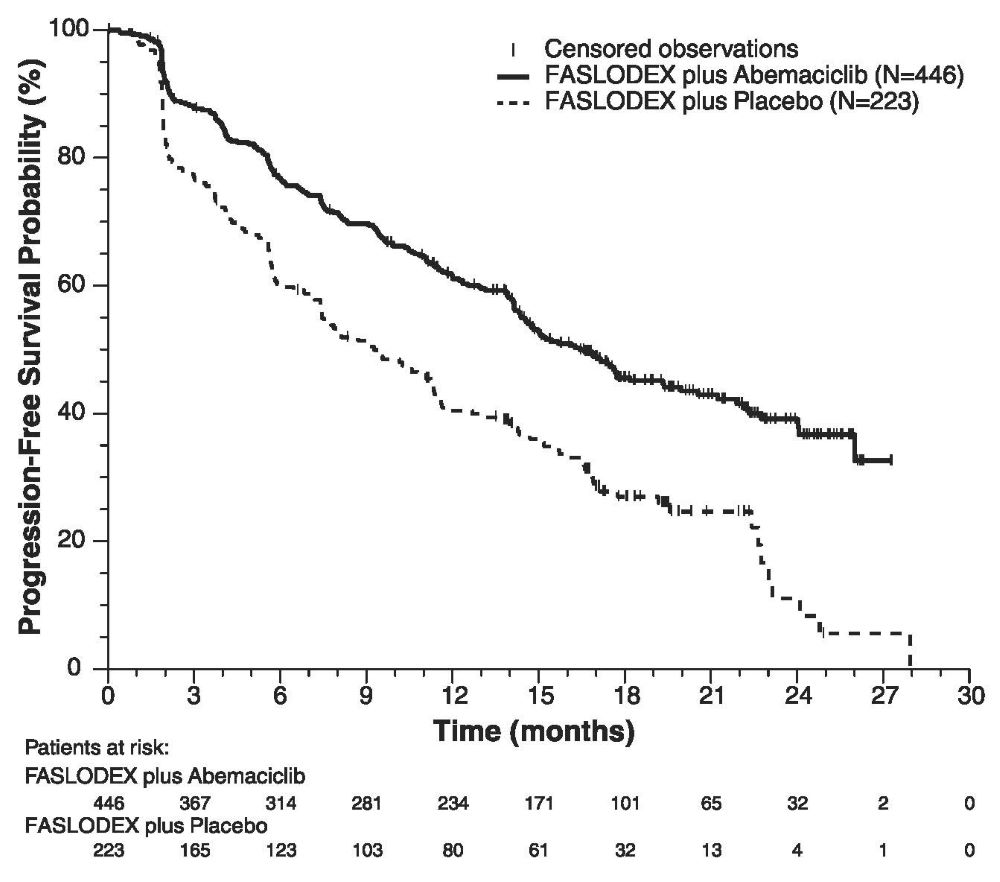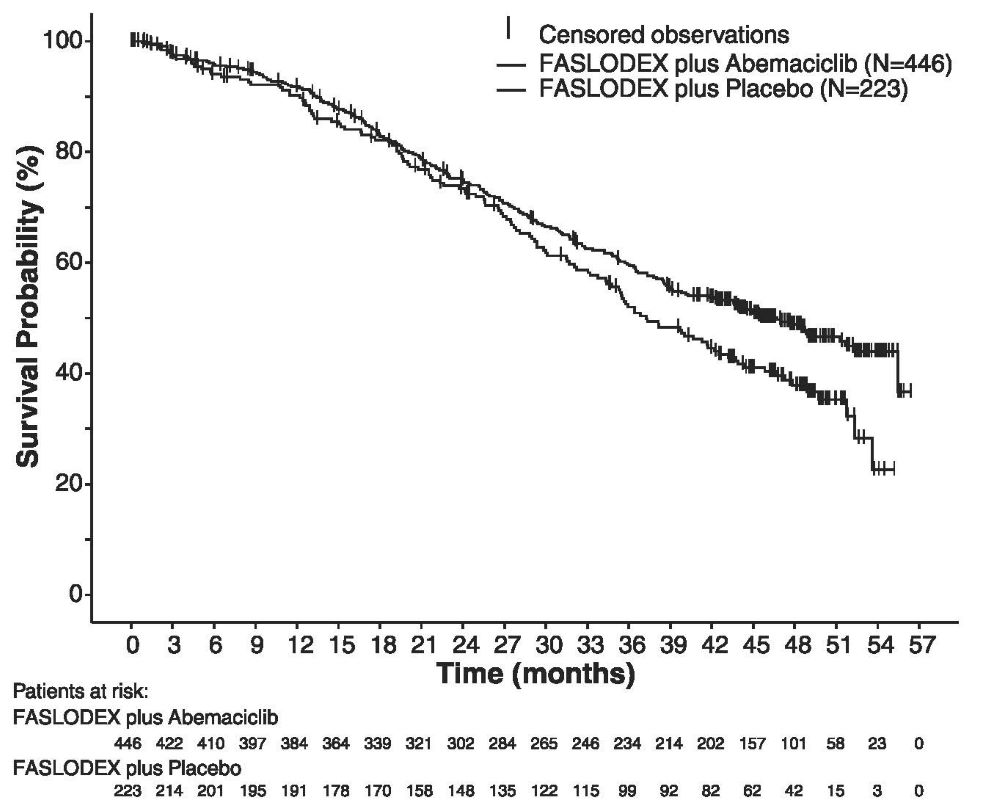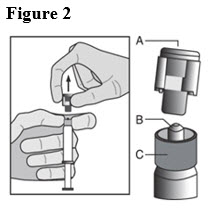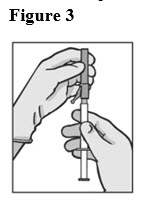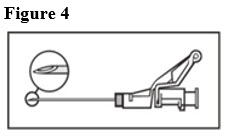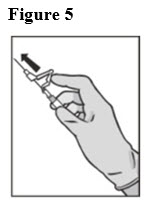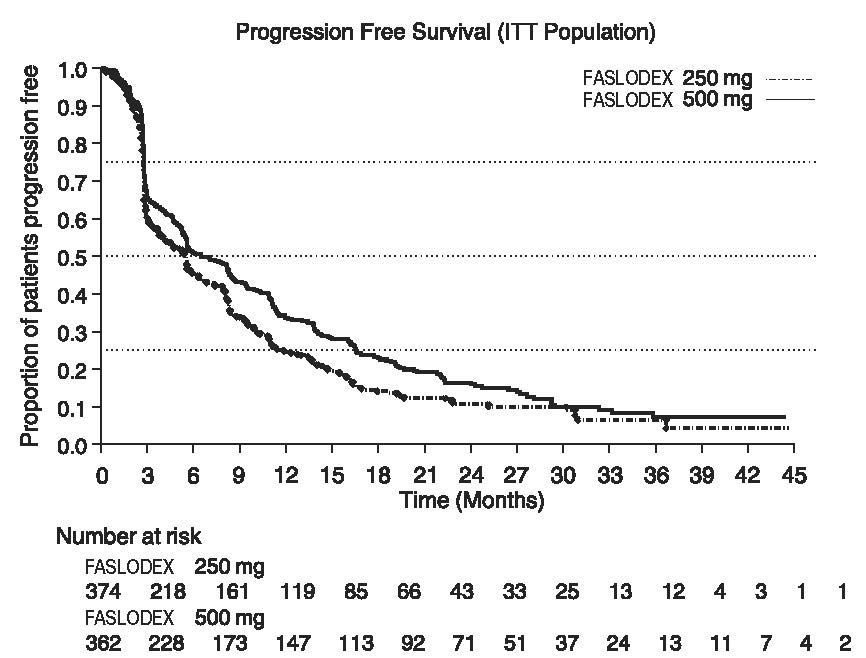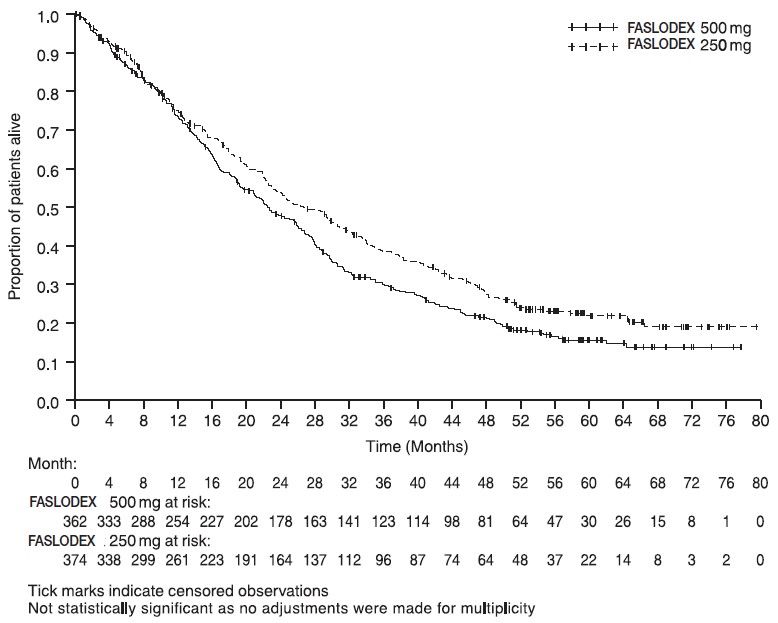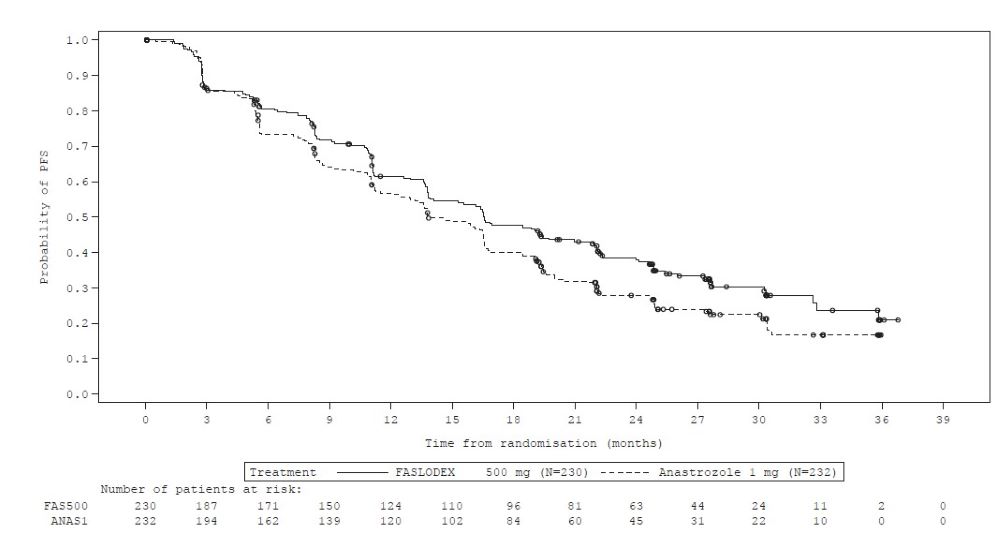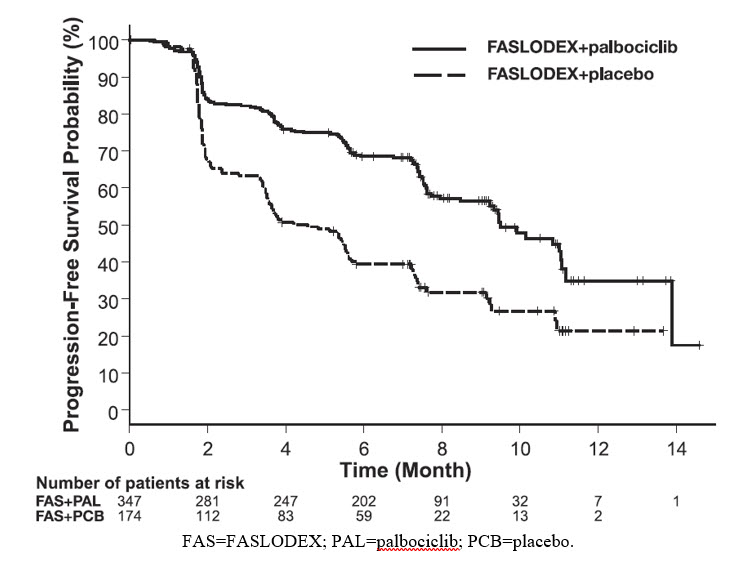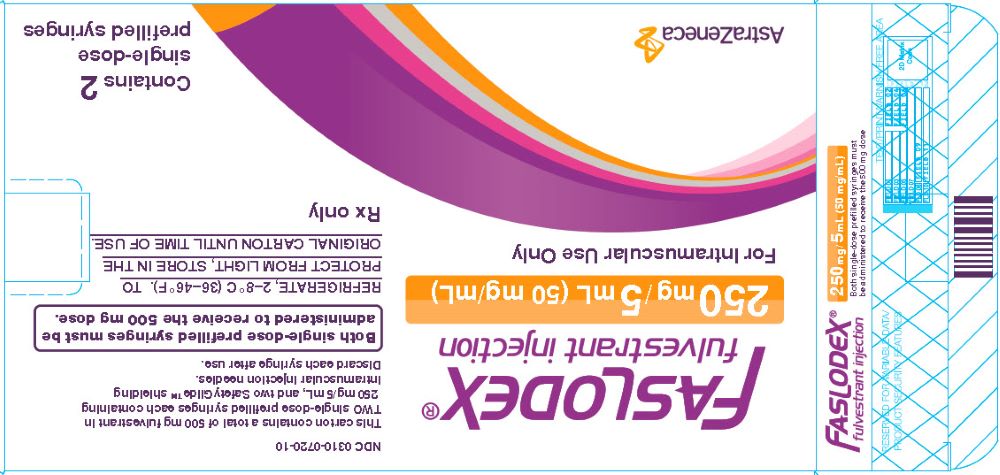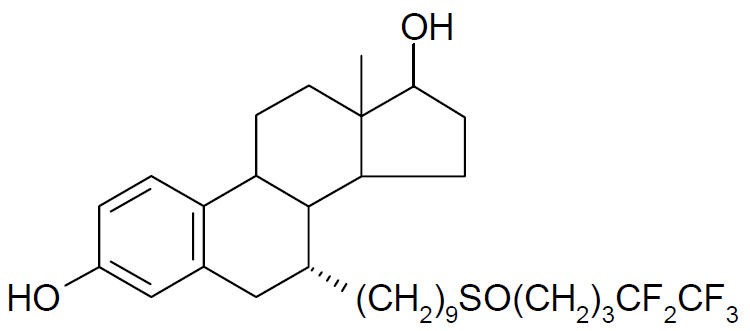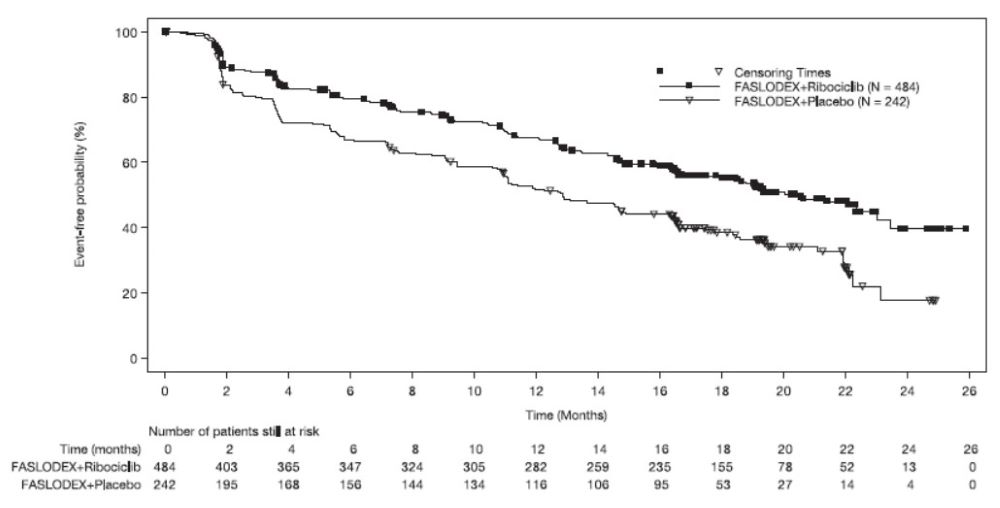 DRUG LABEL: FASLODEX
NDC: 0310-0720 | Form: INJECTION
Manufacturer: AstraZeneca Pharmaceuticals LP
Category: prescription | Type: HUMAN PRESCRIPTION DRUG LABEL
Date: 20200925

ACTIVE INGREDIENTS: FULVESTRANT 50 mg/1 mL
INACTIVE INGREDIENTS: ALCOHOL; BENZYL ALCOHOL; BENZYL BENZOATE; CASTOR OIL

HIGHLIGHTS OF PRESCRIBING INFORMATION

These highlights do not include all the information needed to use FASLODEX safely and effectively. See full prescribing information for FASLODEX.
FASLODEX® (fulvestrant) injection, for intramuscular use
Initial U.S. Approval: 2002

1 INDICATIONS AND USAGE

FASLODEX is an estrogen receptor antagonist indicated for the treatment of:

- Hormone receptor (HR)-positive, human epidermal growth factor receptor 2 (HER2)-negative advanced breast cancer in postmenopausal women not previously treated with endocrine therapy. (1)
- HR-positive advanced breast cancer in postmenopausal women with disease progression following endocrine therapy. (1)
- HR-positive, HER2-negative advanced or metastatic breast cancer in postmenopausal women in combination with ribociclib, as initial endocrine based therapy or following disease progression on endocrine therapy. (1)
- HR-positive, HER2-negative advanced or metastatic breast cancer in combination with palbociclib or abemaciclib in women with disease progression after endocrine therapy. (1)

2 DOSAGE AND ADMINISTRATION

- FASLODEX 500 mg should be administered intramuscularly into the buttocks (gluteal area) slowly (1 - 2 minutes per injection) as two 5 mL injections, one in each buttock, on Days 1, 15, 29, and once monthly thereafter. (2.1, 14)
- A dose of 250 mg is recommended in patients with moderate hepatic impairment to be administered intramuscularly into the buttock (gluteal area) slowly (1 - 2 minutes) as one 5 mL injection on Days 1, 15, 29, and once monthly thereafter. (2.2, 5.2, 8.6)

3 DOSAGE FORMS AND STRENGTHS

FASLODEX, an injection for intramuscular administration, is supplied as 250 mg/5 mL fulvestrant. (3)

4 CONTRAINDICATIONS

- Hypersensitivity. (4)

5 WARNINGS AND PRECAUTIONS

- Risk of Bleeding: Use with caution in patients with bleeding diatheses, thrombocytopenia, or anticoagulant use. (5.1)
- Increased Exposure in Patients with Hepatic Impairment: Use a 250 mg dose for patients with moderate hepatic impairment. (2.2, 5.2, 8.6)
- Injection Site Reaction: Use caution while administering FASLODEX at the dorsogluteal injection site due to the proximity of the underlying sciatic nerve. (5.3)
- Embryo-Fetal Toxicity: Can cause fetal harm. Advise females of reproductive potential of the potential risk to a fetus and to use effective contraception. (5.4, 8.1, 8.3)
- Immunoassay Measurement of Serum Estradiol: FASLODEX can interfere with estradiol measurement by immunoassay, resulting in falsely elevated estradiol levels. (5.5)

6 ADVERSE REACTIONS

- The most common adverse reactions occurring in ≥5% of patients receiving FASLODEX 500 mg were: injection site pain, nausea, bone pain, arthralgia, headache, back pain, fatigue, pain in extremity, hot flash, vomiting, anorexia, asthenia, musculoskeletal pain, cough, dyspnea, and constipation. (6.1)
- Increased hepatic enzymes (ALT, AST, ALP) occurred in >15% of FASLODEX patients and were not dose-dependent. (6.1)

To report SUSPECTED ADVERSE REACTIONS, contact AstraZeneca at 1-800-236-9933 or FDA at 1-800-FDA-1088 or www.fda.gov/medwatch.

7 DRUG INTERACTIONS

- There are no known drug-drug interactions. (7)

8 USE IN SPECIFIC POPULATIONS

- Lactation: Advise not to breastfeed. (8.2)

FULL PRESCRIBING INFORMATION

1 INDICATIONS AND USAGE

Monotherapy

FASLODEX is indicated for the treatment of:

- Hormone receptor (HR)-positive, human epidermal growth factor receptor 2 (HER2)-negative advanced breast cancer in postmenopausal women not previously treated with endocrine therapy, or
- HR-positive advanced breast cancer in postmenopausal women with disease progression following endocrine therapy.

Combination Therapy

FASLODEX is indicated for the treatment of:

- HR-positive, HER2-negative advanced or metastatic breast cancer in postmenopausal women in combination with ribociclib as initial endocrine based therapy or following disease progression on endocrine therapy.
- HR-positive, HER2-negative advanced or metastatic breast cancer in combination with palbociclib or abemaciclib in women with disease progression after endocrine therapy.

2 DOSAGE AND ADMINISTRATION

2.1 Recommended Dose

Monotherapy

The recommended dose of FASLODEX is 500 mg to be administered intramuscularly into the buttocks (gluteal area) slowly (1 - 2 minutes per injection) as two 5 mL injections, one in each buttock, on Days 1, 15, 29, and once monthly thereafter [see Clinical Studies (14)].

Combination Therapy

When FASLODEX is used in combination with palbociclib, abemaciclib, or ribociclib, the recommended dose of FASLODEX is 500 mg to be administered intramuscularly into the buttocks (gluteal area) slowly (1 - 2 minutes per injection) as two 5 mL injections, one in each buttock, on Days 1, 15, 29, and once monthly thereafter.

When FASLODEX is used in combination with palbociclib, the recommended dose of palbociclib is a 125 mg capsule taken orally once daily for 21 consecutive days followed by 7 days off treatment to comprise a complete cycle of 28 days. Palbociclib should be taken with food. Refer to the Full Prescribing Information for palbociclib.

When FASLODEX is used in combination with abemaciclib, the recommended dose of abemaciclib is 150 mg orally, twice daily. Abemaciclib may be taken with or without food. Refer to the Full Prescribing Information for abemaciclib.

When FASLODEX is used in combination with ribociclib, the recommended dose of ribociclib is 600 mg taken orally, once daily for 21 consecutive days followed by 7 days off treatment resulting in a complete cycle of 28 days. Ribociclib can be taken with or without food. Refer to the Full Prescribing Information for ribociclib.

Pre/perimenopausal women treated with the combination of FASLODEX plus palbociclib, abemaciclib, or ribociclib, should be treated with luteinizing hormone-releasing hormone (LHRH) agonists according to current clinical practice standards [see Clinical Studies (14)].

2.2 Dose Modification

Monotherapy

Hepatic Impairment:

A dose of 250 mg is recommended for patients with moderate hepatic impairment (Child-Pugh class B) to be administered intramuscularly into the buttock (gluteal area) slowly (1 - 2 minutes) as one 5 mL injection on Days 1, 15, 29, and once monthly thereafter.

FASLODEX has not been evaluated in patients with severe hepatic impairment (Child-Pugh class C) [see Warnings and Precautions (5.2) and Use in Specific Populations (8.6)].

Combination Therapy

When FASLODEX is used in combination with palbociclib, abemaciclib, or ribociclib, refer to monotherapy dose modification instructions for FASLODEX.

Refer to the Full Prescribing Information of co-administered palbociclib, abemaciclib, or ribociclib for dose modification guidelines in the event of toxicities, for use with concomitant medications, and other relevant safety information.

2.3 Administration Technique

Administer the injection according to the local guidelines for performing large volume intramuscular injections.

NOTE: Due to the proximity of the underlying sciatic nerve, caution should be taken if administering FASLODEX at the dorsogluteal injection site [see Warnings and Precautions (5.3) and Adverse Reactions (6.1)].

The proper method of administration of FASLODEX for intramuscular use is described in the following instructions.

For each single-dose prefilled syringe:

1. Remove glass syringe barrel from tray and check that it is not damaged.
2. Remove perforated patient record label from syringe.
3. Inspect drug product in glass syringe for any visible particulate matter or discoloration prior to use. Discard if particulate matter or discoloration is present.
4. Peel open the safety needle (SafetyGlide™) outer packaging.
5. Hold the syringe upright on the ribbed part (C). With the other hand, take hold of the cap (A) and carefully tilt cap back and forth (DO NOT TWIST CAP) until the cap disconnects for removal (see Figure 1).
6. Pull the cap (A) off in a straight upward direction. DO NOT TOUCH THE STERILE SYRINGE TIP (Luer-Lok) (B) (see Figure 2).

1. Attach the safety needle to the syringe tip (Luer-Lok). Twist needle until firmly seated (see Figure 3). Confirm that the needle is locked to the Luer connector before moving or tilting the syringe out of the vertical plane to avoid spillage of syringe contents.

For Administration:

1. Pull shield straight off needle to avoid damaging needle point.
2. Remove needle sheath.
3. Expel excess gas from the syringe (a small gas bubble may remain).
4. Administer intramuscularly slowly (1-2 minutes/injection) into the buttock (gluteal area). For user convenience, the needle ‘bevel up’ position is orientated to the lever arm, as shown in Figure 4.

1. After injection, immediately activate the lever arm to deploy the needle shielding by applying a single-finger stroke to the activation assisted lever arm to push the lever arm completely forward. Listen for a click. Confirm that the needle shielding has completely covered the needle (see Figure 5).
NOTE: Activate away from self and others.

1. Discard the empty syringe into an approved sharps collector in accordance with applicable regulations and institutional policy.
2. Repeat steps 1 through 13 for second syringe.

How To Use FASLODEX

For the 2 x 5 mL syringe package, the contents of both syringes must be injected to receive the 500 mg recommended dose.

SAFETYGLIDE™ INSTRUCTIONS FROM BECTON DICKINSON

SafetyGlide™ is a trademark of Becton Dickinson and Company.

Important Administration Information

To help avoid HIV (AIDS), HBV (Hepatitis), and other infectious diseases due to accidental needlesticks, contaminated needles should not be recapped or removed, unless there is no alternative or that such action is required by a specific medical procedure. Hands must remain behind the needle at all times during use and disposal.

Do not autoclave SafetyGlide™ Needle before use.

Becton Dickinson guarantees the contents of their unopened or undamaged packages to be sterile, non-toxic, and non-pyrogenic.

3 DOSAGE FORMS AND STRENGTHS

FASLODEX, an injection for intramuscular administration, is supplied as 5-mL single-dose prefilled syringes containing 250 mg/5 mL fulvestrant.

4 CONTRAINDICATIONS

FASLODEX is contraindicated in patients with a known hypersensitivity to the drug or to any of its components. Hypersensitivity reactions, including urticaria and angioedema, have been reported in association with FASLODEX [see Adverse Reactions (6.2)].

5 WARNINGS AND PRECAUTIONS

5.1 Risk of Bleeding

Because FASLODEX is administered intramuscularly, it should be used with caution in patients with bleeding diatheses, thrombocytopenia, or anticoagulant use.

5.2 Increased Exposure in Patients with Hepatic Impairment

The safety and pharmacokinetics of FASLODEX were evaluated in a study in seven subjects with moderate hepatic impairment (Child-Pugh class B) and seven subjects with normal hepatic function. Exposure was increased in patients with moderate hepatic impairment, therefore, a dose of 250 mg is recommended [see Dosage and Administration (2.2)].

FASLODEX has not been studied in patients with severe hepatic impairment (Child-Pugh class C) [see Use in Specific Populations (8.6)].

5.3 Injection Site Reaction

Injection site related events including sciatica, neuralgia, neuropathic pain, and peripheral neuropathy have been reported with FASLODEX injection. Caution should be taken while administering FASLODEX at the dorsogluteal injection site due to the proximity of the underlying sciatic nerve [see Dosage and Administration (2.3) and Adverse Reactions (6.1)].

5.4 Embryo-Fetal Toxicity

Based on findings from animal studies and its mechanism of action, FASLODEX can cause fetal harm when administered to a pregnant woman. In animal reproduction studies, administration of fulvestrant to pregnant rats and rabbits during organogenesis resulted in embryo-fetal toxicity at daily doses that are significantly less than the maximum recommended human dose. Advise pregnant women of the potential risk to a fetus. Advise females of reproductive potential to use effective contraception during treatment with FASLODEX and for one year after the last dose [see Use in Specific Populations (8.1), (8.3) and Clinical Pharmacology (12.1)].

5.5 Immunoassay Measurement of Serum Estradiol

Due to structural similarity of fulvestrant and estradiol, FASLODEX can interfere with estradiol measurement by immunoassay, resulting in falsely elevated estradiol levels.

6 ADVERSE REACTIONS

The following adverse reactions are discussed in more detail in other sections of the labeling:

- Risk of Bleeding [see Warnings and Precautions (5.1)]
- Increased Exposure in Patients with Hepatic Impairment [see Warnings and Precautions (5.2)]
- Injection Site Reaction [see Warnings and Precautions (5.3)]
- Embryo-Fetal Toxicity [see Warnings and Precautions (5.4)]

6.1 Clinical Trials Experience

Because clinical trials are conducted under widely varying conditions, the adverse reaction rates observed cannot be directly compared to rates in other trials and may not reflect the rates observed in clinical practice.

Monotherapy

Comparison of FASLODEX 500 mg and FASLODEX 250 mg (CONFIRM)

The following adverse reactions (ARs) were calculated based on the safety analysis of CONFIRM comparing the administration of FASLODEX 500 mg intramuscularly once a month with FASLODEX 250 mg intramuscularly once a month. The most frequently reported adverse reactions in the FASLODEX 500 mg group were injection site pain (11.6% of patients), nausea (9.7% of patients), and bone pain (9.4% of patients); the most frequently reported adverse reactions in the FASLODEX 250 mg group were nausea (13.6% of patients), back pain (10.7% of patients), and injection site pain (9.1% of patients).

Table 1 lists adverse reactions reported with an incidence of 5% or greater, regardless of assessed causality, from CONFIRM.

Table 1: Adverse Reactions in CONFIRM (≥5% in Either Treatment Group)
Adverse Reactions | FASLODEX 500 mg; N=361; % | FASLODEX 250 mg; N=374; %
Body as a Whole
Injection Site Pain [Including more severe injection site related sciatica, neuralgia, neuropathic pain, and peripheral neuropathy.] | 12 | 9
Headache | 8 | 7
Back Pain | 8 | 11
Fatigue | 8 | 6
Pain in Extremity | 7 | 7
Asthenia | 6 | 6
Vascular System
Hot Flash | 7 | 6
Digestive System
Nausea | 10 | 14
Vomiting | 6 | 6
Anorexia | 6 | 4
Constipation | 5 | 4
Musculoskeletal System
Bone Pain | 9 | 8
Arthralgia | 8 | 8
Musculoskeletal Pain | 6 | 3
Respiratory System
Cough | 5 | 5
Dyspnea | 4 | 5

In the pooled safety population (N=1127) from clinical trials comparing FASLODEX 500 mg to FASLODEX 250 mg, post-baseline increases of ≥1 CTC grade in either AST, ALT, or alkaline phosphatase were observed in >15% of patients receiving FASLODEX. Grade 3-4 increases were observed in 1-2% of patients. The incidence and severity of increased hepatic enzymes (ALT, AST, ALP) did not differ between the 250 mg and the 500 mg FASLODEX arms.

Comparison of FASLODEX 500 mg and Anastrozole 1 mg (FALCON)

The safety of FASLODEX 500 mg versus anastrozole 1 mg was evaluated in FALCON. The data described below reflect exposure to FASLODEX in 228 out of 460 patients with HR-positive advanced breast cancer in postmenopausal women not previously treated with endocrine therapy who received at least one (1) dose of treatment in FALCON.

Permanent discontinuation associated with an adverse reaction occurred in 4 of 228 (1.8%) patients receiving FASLODEX and in 3 of 232 (1.3%) patients receiving anastrozole. Adverse reactions leading to discontinuation for those patients receiving FASLODEX included drug hypersensitivity (0.9%), injection site hypersensitivity (0.4%), and elevated liver enzymes (0.4%).

The most common adverse reactions (≥10%) of any grade reported in patients in the FASLODEX arm were arthralgia, hot flash, fatigue, and nausea.

Adverse reactions reported in patients who received FASLODEX in FALCON at an incidence of ≥5% in either treatment arm are listed in Table 2, and laboratory abnormalities are listed in Table 3.

Table 2: Adverse Reactions in FALCON
Adverse Reactions | FASLODEX 500 mg; N=228 |  | Anastrozole 1 mg; N=232
Adverse Reactions | All Grades; % | Grade 3 or 4; % | All Grades; % | Grade 3 or 4; %
Vascular Disorders
Hot flash | 11 | 0 | 10 | 0
Gastrointestinal Disorders
Nausea | 11 | 0 | 10 | <1
Diarrhea | 6 | 0 | 6 | <1
Musculoskeletal and Connective Tissue Disorders
Arthralgia | 17 | 0 | 10 | 0
Myalgia | 7 | 0 | 3 | 0
Pain in extremity | 6 | 0 | 4 | 0
Back pain | 9 | <1 | 6 | 0
General Disorders and Administration Site Conditions
Fatigue | 11 | <1 | 7 | <1

Table 3: Laboratory Abnormalities in FALCON [In FALCON, post-baseline increases of ≥1 CTC grade in either AST, ALT, or alkaline phosphatase were observed in >10% of patients receiving FASLODEX. Grade 3-4 increases were observed in 1%-3% of patients.]
Laboratory Parameters | FASLODEX 500 mg; N=228 |  | Anastrozole 1 mg; N=232
Laboratory Parameters | All Grades; % | Grade 3 or 4; % | All Grades; % | Grade 3 or 4; %
Alanine aminotransferase increased (ALT) | 7 | 1 | 3 | 0
Aspartate aminotransferase increased (AST) | 5 | 1 | 3 | <1

Comparison of FASLODEX 250 mg and Anastrozole 1 mg in Combined Trials (Studies 0020 and 0021)

The most commonly reported adverse reactions in the FASLODEX and anastrozole treatment groups were gastrointestinal symptoms (including nausea, vomiting, constipation, diarrhea, and abdominal pain), headache, back pain, vasodilatation (hot flashes), and pharyngitis.

Injection site reactions with mild transient pain and inflammation were seen with FASLODEX and occurred in 7% of patients given the single 5 mL injection (Study 0020) and in 27% of patients given the 2 x 2.5 mL injections (Study 0021) in the two clinical trials that compared FASLODEX 250 mg and anastrozole 1 mg.

Table 4 lists adverse reactions reported with an incidence of 5% or greater, regardless of assessed causality, from the two controlled clinical trials comparing the administration of FASLODEX 250 mg intramuscularly once a month with anastrozole 1 mg orally once a day.

Table 4: Adverse Reactions in Studies 0020 and 0021 (≥5% from Combined Data)
Adverse Reactions | FASLODEX 250 mg N=423 % | Anastrozole 1 mg N=423 %
Body as a Whole | 68 | 68
Asthenia | 23 | 27
Pain | 19 | 20
Headache | 15 | 17
Back Pain | 14 | 13
Abdominal Pain | 12 | 12
Injection Site Pain [Including more severe injection site related sciatica, neuralgia, neuropathic pain, and peripheral neuropathy. All patients on FASLODEX received injections, but only those anastrozole patients who were in Study 0021 received placebo injections.] | 11 | 7
Pelvic Pain | 10 | 9
Chest Pain | 7 | 5
Flu Syndrome | 7 | 6
Fever | 6 | 6
Accidental Injury | 5 | 6
Cardiovascular System | 30 | 28
Vasodilatation | 18 | 17
Digestive System | 52 | 48
Nausea | 26 | 25
Vomiting | 13 | 12
Constipation | 13 | 11
Diarrhea | 12 | 13
Anorexia | 9 | 11
Hemic and Lymphatic Systems | 14 | 14
Anemia | 5 | 5
Metabolic and Nutritional Disorders | 18 | 18
Peripheral Edema | 9 | 10
Musculoskeletal System | 26 | 28
Bone Pain | 16 | 14
Arthritis | 3 | 6
Nervous System | 34 | 34
Dizziness | 7 | 7
Insomnia | 7 | 9
Paresthesia | 6 | 8
Depression | 6 | 7
Anxiety | 5 | 4
Respiratory System | 39 | 34
Pharyngitis | 16 | 12
Dyspnea | 15 | 12
Cough Increased | 10 | 10
Skin and Appendages | 22 | 23
Rash | 7 | 8
Sweating | 5 | 5
Urogenital System | 18 | 15
Urinary Tract Infection | 6 | 4

Combination Therapy

Combination Therapy with Palbociclib (PALOMA-3)

The safety of FASLODEX 500 mg plus palbociclib 125 mg/day versus FASLODEX plus placebo was evaluated in PALOMA-3. The data described below reflect exposure to FASLODEX plus palbociclib in 345 out of 517 patients with HR-positive, HER2-negative advanced or metastatic breast cancer who received at least 1 dose of treatment in PALOMA-3. The median duration of treatment for FASLODEX plus palbociclib was 10.8 months while the median duration of treatment for FASLODEX plus placebo arm was 4.8 months.

No dose reduction was allowed for FASLODEX in PALOMA-3. Dose reductions of palbociclib due to an adverse reaction of any grade occurred in 36% of patients receiving FASLODEX plus palbociclib.

Permanent discontinuation associated with an adverse reaction occurred in 19 of 345 (6%) patients receiving FASLODEX plus palbociclib, and in 6 of 172 (3%) patients receiving FASLODEX plus placebo. Adverse reactions leading to discontinuation for those patients receiving FASLODEX plus palbociclib included fatigue (0.6%), infections (0.6%), and thrombocytopenia (0.6%).

The most common adverse reactions (≥10%) of any grade reported in patients in the FASLODEX plus palbociclib arm by descending frequency were neutropenia, leukopenia, infections, fatigue, nausea, anemia, stomatitis, diarrhea, thrombocytopenia, vomiting, alopecia, rash, decreased appetite, and pyrexia.

The most frequently reported Grade ≥3 adverse reactions (≥5%) in patients receiving FASLODEX plus palbociclib in descending frequency were neutropenia and leukopenia.

Adverse reactions (≥10%) reported in patients who received FASLODEX plus palbociclib or FASLODEX plus placebo in PALOMA-3 are listed in Table 5, and laboratory abnormalities are listed in Table 6.

Table 5: Adverse Reactions (≥10%) in PALOMA-3
Adverse Reactions | FASLODEX plus Palbociclib N=345 |  |  | FASLODEX plus Placebo N=172
Adverse Reactions | All Grades % | Grade 3 % | Grade 4 % | All Grades % | Grade 3 % | Grade 4 %
Infections and Infestations
Infections [Infections includes all reported preferred terms (PTs) that are part of the System Organ Class Infections and infestations.] | 47 [Most common infections (≥1%) include: nasopharyngitis, upper respiratory infection, urinary tract infection, influenza, bronchitis, rhinitis, conjunctivitis, pneumonia, sinusitis, cystitis, oral herpes, respiratory tract infection, gastroenteritis, tooth infection, pharyngitis, eye infection, herpes simplex, paronychia.] | 3 | 1 | 31 | 3 | 0
Blood and Lymphatic System Disorders
Neutropenia | 83 | 55 | 11 | 4 | 1 | 0
Leukopenia | 53 | 30 | 1 | 5 | 1 | 1
Anemia | 30 | 4 | 0 | 13 | 2 | 0
Thrombocytopenia | 23 | 2 | 1 | 0 | 0 | 0
Metabolism and Nutrition Disorders
Decreased appetite | 16 | 1 | 0 | 8 | 1 | 0
Gastrointestinal Disorders
Nausea | 34 | 0 | 0 | 28 | 1 | 0
Stomatitis [Stomatitis includes: aphthous stomatitis, cheilitis, glossitis, glossodynia, mouth ulceration, mucosal inflammation, oral pain, oropharyngeal discomfort, oropharyngeal pain, stomatitis.] | 28 | 1 | 0 | 13 | 0 | 0
Diarrhea | 24 | 0 | 0 | 19 | 1 | 0
Vomiting | 19 | 1 | 0 | 15 | 1 | 0
Skin and Subcutaneous Tissue Disorders
Alopecia | 18 [Grade 1 events – 17%; Grade 2 events – 1%.] | N/A | N/A | 6 [Grade 1 events – 6%.] | N/A | N/A
Rash [Rash includes: rash, rash maculo-papular, rash pruritic, rash erythematous, rash papular, dermatitis, dermatitis acneiform, toxic skin eruption.] | 17 | 1 | 0 | 6 | 0 | 0
General Disorders and Administration Site Conditions
Fatigue | 41 | 2 | 0 | 29 | 1 | 0
Pyrexia | 13 | <1 | 0 | 5 | 0 | 0
Grading according to CTCAE v.4.0.
CTCAE=Common Terminology Criteria for Adverse Events; N=number of patients; N/A=not applicable.

Additional adverse reactions occurring at an overall incidence of <10.0% of patients receiving FASLODEX plus palbociclib in PALOMA-3 included asthenia (7.5%), aspartate aminotransferase increased (7.5%), dysgeusia (6.7%), epistaxis (6.7%), lacrimation increased (6.4%), dry skin (6.1%), alanine aminotransferase increased (5.8%), vision blurred (5.8%), dry eye (3.8%), and febrile neutropenia (0.9%).

Table 6: Laboratory Abnormalities in PALOMA-3
Laboratory Parameters | FASLODEX plus Palbociclib N=345 |  |  | FASLODEX plus Placebo N=172
Laboratory Parameters | All Grades % | Grade 3 % | Grade 4 % | All Grades % | Grade 3 % | Grade 4 %
WBC decreased | 99 | 45 | 1 | 26 | 0 | 1
Neutrophils decreased | 96 | 56 | 11 | 14 | 0 | 1
Anemia | 78 | 3 | 0 | 40 | 2 | 0
Platelets decreased | 62 | 2 | 1 | 10 | 0 | 0
Aspartate aminotransferase increased | 43 | 4 | 0 | 48 | 4 | 0
Alanine aminotransferase increased | 36 | 2 | 0 | 34 | 0 | 0

N=number of patients; WBC=white blood cells.

Combination Therapy with Abemaciclib (MONARCH 2)

The safety of FASLODEX (500 mg) plus abemaciclib (150 mg twice daily) versus FASLODEX plus placebo was evaluated in MONARCH 2. The data described below reflect exposure to FASLODEX in 664 patients with HR-positive, HER2-negative advanced breast cancer who received at least one dose of FASLODEX plus abemaciclib or placebo in MONARCH 2.

Median duration of treatment was 12 months for patients receiving FASLODEX plus abemaciclib and 8 months for patients receiving FASLODEX plus placebo.

Dose reductions due to an adverse reaction occurred in 43% of patients receiving FASLODEX plus abemaciclib. Adverse reactions leading to dose reductions ≥5% of patients were diarrhea and neutropenia. Abemaciclib dose reduction due to diarrhea of any grade occurred in 19% of patients receiving FASLODEX plus abemaciclib compared to 0.4% of patients receiving FASLODEX plus placebo. Abemaciclib dose reductions due to neutropenia of any grade occurred in 10% of patients receiving FASLODEX plus abemaciclib compared to no patients receiving FASLODEX plus placebo.

Permanent study treatment discontinuation due to an adverse event was reported in 9% of patients receiving FASLODEX plus abemaciclib and in 3% of patients receiving FASLODEX plus placebo. Adverse reactions leading to permanent discontinuation for patients receiving FASLODEX plus abemaciclib were infection (2%), diarrhea (1%), hepatotoxicity (1%), fatigue (0.7%), nausea (0.2%), abdominal pain (0.2%), acute kidney injury (0.2%), and cerebral infarction (0.2%).

Deaths during treatment or during the 30-day follow up, regardless of causality, were reported in 18 cases (4%) of FASLODEX plus abemaciclib treated patients versus 10 cases (5%) of FASLODEX plus placebo treated patients. Causes of death for patients receiving FASLODEX plus abemaciclib included: 7 (2%) patient deaths due to underlying disease, 4 (0.9%) due to sepsis, 2 (0.5%) due to pneumonitis, 2 (0.5%) due to hepatotoxicity, and one (0.2%) due to cerebral infarction.

The most common adverse reactions reported (≥20%) in the FASLODEX plus abemaciclib arm were diarrhea, fatigue, neutropenia, nausea, infections, abdominal pain, anemia, leukopenia, decreased appetite, vomiting, and headache (Table 7). The most frequently reported (≥5%) Grade 3 or 4 adverse reactions were neutropenia, diarrhea, leukopenia, anemia, and infections.

Table 7: Adverse Reactions ≥10% of Patients Receiving FASLODEX Plus Abemaciclib and ≥2% Higher Than FASLODEX Plus Placebo in MONARCH 2
Adverse Reactions | FASLODEX plus Abemaciclib; N=441 |  |  | FASLODEX plus Placebo; N=223
 | All Grades; % | Grade; 3; % | Grade 4; % | All Grades; % | Grade; 3; % | Grade 4; %
Gastrointestinal Disorders
Diarrhea | 86 | 13 | 0 | 25 | <1 | 0
Nausea | 45 | 3 | 0 | 23 | 1 | 0
Abdominal pain [Includes abdominal pain, abdominal pain upper, abdominal pain lower, abdominal discomfort, abdominal tenderness.] | 35 | 2 | 0 | 16 | 1 | 0
Vomiting | 26 | <1 | 0 | 10 | 2 | 0
Stomatitis | 15 | <1 | 0 | 10 | 0 | 0
Infections and Infestations
Infections [Includes upper respiratory tract infection, urinary tract infection, lung infection, pharyngitis, conjunctivitis, sinusitis, vaginal infection, sepsis.] | 43 | 5 | <1 | 25 | 3 | <1
Blood and Lymphatic System Disorders
Neutropenia [Includes neutropenia, neutrophil count decreased.] | 46 | 24 | 3 | 4 | 1 | <1
Anemia [Includes anemia, hematocrit decreased, hemoglobin decreased, red blood cell count decreased.] | 29 | 7 | <1 | 4 | 1 | 0
Leukopenia [Includes leukopenia, white blood cell count decreased.] | 28 | 9 | <1 | 2 | 0 | 0
Thrombocytopenia [Includes platelet count decreased, thrombocytopenia.] | 16 | 2 | 1 | 3 | 0 | <1
General Disorders and Administration Site Conditions
Fatigue [Includes asthenia, fatigue.] | 46 | 3 | 0 | 32 | <1 | 0
Edema peripheral | 12 | 0 | 0 | 7 | 0 | 0
Pyrexia | 11 | <1 | <1 | 6 | <1 | 0
Metabolism and Nutrition Disorders
Decreased appetite | 27 | 1 | 0 | 12 | <1 | 0
Respiratory, Thoracic, and Mediastinal Disorders
Cough | 13 | 0 | 0 | 11 | 0 | 0
Skin and Subcutaneous Tissue Disorders
Alopecia | 16 | 0 | 0 | 2 | 0 | 0
Pruritus | 13 | 0 | 0 | 6 | 0 | 0
Rash | 11 | 1 | 0 | 4 | 0 | 0
Nervous System Disorders
Headache | 20 | 1 | 0 | 15 | <1 | 0
Dysgeusia | 18 | 0 | 0 | 3 | 0 | 0
Dizziness | 12 | 1 | 0 | 6 | 0 | 0
Investigations
Alanine aminotransferase increased | 13 | 4 | <1 | 5 | 2 | 0
Aspartate aminotransferase increased | 12 | 2 | 0 | 7 | 3 | 0
Creatinine increased | 12 | <1 | 0 | <1 | 0 | 0
Weight decreased | 10 | <1 | 0 | 2 | <1 | 0

Additional adverse reactions in MONARCH 2 include venous thromboembolic events (deep vein thrombosis, pulmonary embolism, cerebral venous sinus thrombosis, subclavian vein thrombosis, axillary vein thrombosis, and DVT inferior vena cava), which were reported in 5% of patients treated with FASLODEX plus abemaciclib as compared to 0.9% of patients treated with FASLODEX plus placebo.

Table 8: Laboratory Abnormalities ≥10% in Patients Receiving FASLODEX Plus Abemaciclib and ≥2% Higher Than FASLODEX Plus Placebo in MONARCH 2
Laboratory Parameters | Fulvestrant plus Abemaciclib N=441 |  |  | Fulvestrant plus Placebo N=223
 | All Grades % | Grade 3 % | Grade 4 % | All Grades % | Grade 3 % | Grade 4 %
Creatinine increased | 98 | 1 | 0 | 74 | 0 | 0
White blood cell decreased | 90 | 23 | <1 | 33 | <1 | 0
Neutrophil count decreased | 87 | 29 | 4 | 30 | 4 | <1
Anemia | 84 | 3 | 0 | 33 | <1 | 0
Lymphocyte count decreased | 63 | 12 | <1 | 32 | 2 | 0
Platelet count decreased | 53 | <1 | 1 | 15 | 0 | 0
Alanine aminotransferase increased | 41 | 4 | <1 | 32 | 1 | 0
Aspartate aminotransferase increased | 37 | 4 | 0 | 25 | 4 | <1

Combination Therapy with Ribociclib (MONALEESA-3)

The safety of FASLODEX 500 mg plus ribociclib 600 mg versus FASLODEX plus placebo was evaluated in MONALEESA-3. The data described below reflect exposure to FASLODEX plus ribociclib in 483 out of 724 postmenopausal patients with HR-positive, HER2-negative advanced or metastatic breast cancer for initial endocrine based therapy or after disease progression on endocrine therapy who received at least one dose of FASLODEX plus ribociclib or placebo in MONALEESA-3. Median duration of treatment was 15.8 months for FASLODEX plus ribociclib and 12 months for FASLODEX plus placebo.

Dose reductions due to adverse reactions occurred in 32% of patients receiving FASLODEX plus ribociclib and in 3% of patients receiving FASLODEX plus placebo. Among patients receiving FASLODEX plus ribociclib, 8% were reported to have permanently discontinued both FASLODEX plus ribociclib, and 9% were reported to have discontinued ribociclib alone due to ARs. Among patients receiving FASLODEX plus placebo, 4% were reported to have permanently discontinued both FASLODEX and placebo and 2% were reported to have discontinued placebo alone due to ARs.

Adverse reactions leading to treatment discontinuation of FASLODEX plus ribociclib (as compared to FASLODEX plus placebo) were ALT increased (5% vs. 0%), AST increased (3% vs. 0.6%), and vomiting (1% vs. 0%).

The most common adverse reactions (reported at a frequency ≥20% on the FASLODEX plus ribociclib arm and ≥2% higher than FASLODEX plus placebo) were neutropenia, infections, leukopenia, cough, nausea, diarrhea, vomiting, constipation, pruritus, and rash. The most frequently reported Grade 3/4 adverse reactions (reported at a frequency ≥5%) in patients receiving FASLODEX plus ribociclib in descending frequency were neutropenia, leukopenia, infections, and abnormal liver function tests.

Adverse reactions and laboratory abnormalities occurring in patients in MONALEESA-3 are listed in Table 9 and Table 10, respectively.

Table 9: Adverse Reactions Occurring in ≥10% and ≥2% higher than FASLODEX plus Placebo Arm in MONALEESA-3 (All Grades)
Adverse Reactions | FASLODEX plus Ribociclib; N=483 |  |  | FASLODEX plus Placebo; N=241
Adverse Reactions | All Grades; % | Grade 3; % | Grade 4; % | All Grades; % | Grade 3; % | Grade 4; %
Infections and Infestations
Infections [Infections; urinary tract infections; respiratory tract infections; gastroenteritis; sepsis (<1%).] | 42 | 5 | 0 | 30 | 2 | 0
Blood and Lymphatic System Disorders
Neutropenia | 69 | 46 | 7 | 2 | 0 | 0
Leukopenia | 27 | 12 | <1 | <1 | 0 | 0
Anemia | 17 | 3 | 0 | 5 | 2 | 0
Metabolism and Nutrition Disorders
Decreased appetite | 16 | <1 | 0 | 13 | 0 | 0
Nervous System Disorders
Dizziness | 13 | <1 | 0 | 8 | 0 | 0
Respiratory, Thoracic, and Mediastinal Disorders
Cough | 22 | 0 | 0 | 15 | 0 | 0
Dyspnea | 15 | 1 | <1 | 12 | 2 | 0
Gastrointestinal Disorders
Nausea | 45 | 1 | 0 | 28 | <1 | 0
Diarrhea | 29 | <1 | 0 | 20 | <1 | 0
Vomiting | 27 | 1 | 0 | 13 | 0 | 0
Constipation | 25 | <1 | 0 | 12 | 0 | 0
Abdominal pain | 17 | 1 | 0 | 13 | <1 | 0
Skin and Subcutaneous Tissue Disorders
Alopecia | 19 | 0 | 0 | 5 | 0 | 0
Pruritus | 20 | <1 | 0 | 7 | 0 | 0
Rash | 23 | <1 | 0 | 7 | 0 | 0
General Disorders and Administration Site Conditions
Edema peripheral | 15 | 0 | 0 | 7 | 0 | 0
Pyrexia | 11 | <1 | 0 | 7 | 0 | 0
Investigations
Alanine aminotransferase increased | 15 | 7 | 2 | 5 | <1 | 0
Aspartate aminotransferase increased | 13 | 5 | 1 | 5 | <1 | 0
Grading according to CTCAE 4.03.
CTCAE=Common Terminology Criteria for Adverse Events; N=number of patients

Additional adverse reactions in MONALEESA-3 for patients receiving FASLODEX plus ribociclib included asthenia (14%), dyspepsia (10%), thrombocytopenia (9%), dry skin (8%), dysgeusia (7%), electrocardiogram QT prolonged (6%), dry mouth (5%), vertigo (5%), dry eye (5%), lacrimation increased (4%), erythema (4%), hypocalcemia (4%), blood bilirubin increased (1%), and syncope (1%).

Table 10: Laboratory Abnormalities Occurring in ≥10% of Patients in MONALEESA-3
Laboratory parameters | FASLODEX plus Ribociclib N=483 |  |  | FASLODEX plus Placebo N=241
Laboratory parameters | All Grades % | Grade 3 % | Grade 4 % | All Grades % | Grade 3 % | Grade 4 %
Hematology
Leukocyte count decreased | 95 | 25 | <1 | 26 | <1 | 0
Neutrophil count decreased | 92 | 46 | 7 | 21 | <1 | 0
Hemoglobin decreased | 60 | 4 | 0 | 35 | 3 | 0
Lymphocyte count decreased | 69 | 14 | 1 | 35 | 4 | <1
Platelet count decreased | 33 | <1 | 1 | 11 | 0 | 0
Chemistry
Creatinine increased | 65 | <1 | <1 | 33 | <1 | 0
Gamma-glutamyl transferase increased | 52 | 6 | 1 | 49 | 8 | 2
Aspartate aminotransferase increased | 49 | 5 | 2 | 43 | 3 | 0
Alanine aminotransferase increased | 44 | 8 | 3 | 37 | 2 | 0
Glucose serum decreased | 23 | 0 | 0 | 18 | 0 | 0
Phosphorous decreased | 18 | 5 | 0 | 8 | <1 | 0
Albumin decreased | 12 | 0 | 0 | 8 | 0 | 0

6.2 Postmarketing Experience

The following adverse reactions have been identified during post-approval use of FASLODEX. Because these reactions are reported voluntarily from a population of uncertain size, it is not always possible to reliably estimate their frequency or establish a causal relationship to drug exposure.

For FASLODEX 250 mg, other adverse reactions reported as drug-related and seen infrequently (<1%) include thromboembolic phenomena, myalgia, vertigo, leukopenia, and hypersensitivity reactions, including angioedema and urticaria.

Vaginal bleeding has been reported infrequently (<1%), mainly in patients during the first 6 weeks after changing from existing hormonal therapy to treatment with FASLODEX. If bleeding persists, further evaluation should be considered.

Elevation of bilirubin, elevation of gamma GT, hepatitis, and liver failure have been reported infrequently (<1%).

7 DRUG INTERACTIONS

There are no known drug-drug interactions. Although, fulvestrant is metabolized by CYP 3A4 in vitro, drug interactions studies with ketoconazole or rifampin did not alter fulvestrant pharmacokinetics. Dose adjustment is not needed in patients co-prescribed CYP 3A4 inhibitors or inducers [see Clinical Pharmacology (12.3)].

8 USE IN SPECIFIC POPULATIONS

8.1 Pregnancy

Risk Summary

Based on findings from animal studies and its mechanism of action, FASLODEX can cause fetal harm when administered to a pregnant woman [see Clinical Pharmacology (12.1)]. There are no available data in pregnant women to inform the drug-associated risk. In animal reproduction studies, administration of fulvestrant to pregnant rats and rabbits during organogenesis caused embryo-fetal toxicity, including skeletal malformations and fetal loss, at daily doses that were 6% and 30% of the maximum recommended human dose based on mg/m^2, respectively [see Data]. Advise pregnant women of the potential risk to a fetus.

The estimated background risk of major birth defects and miscarriage for the indicated population is unknown. In the U.S. general population, the estimated background risk of major birth defects and miscarriage in clinically recognized pregnancies is 2-4% and 15-20%, respectively.

Data

Animal Data

Administration of fulvestrant to rats prior to and up to implantation caused embryonic loss at daily doses that were 0.6% of the daily maximum recommended human dose based on mg/m^2. When fulvestrant was administered to pregnant rats during the period of organogenesis, intramuscular doses ≥0.1 mg/kg/day (6% of the human recommended dose based on mg/m^2) caused effects on embryo-fetal development consistent with its antiestrogenic activity. Fulvestrant caused an increased incidence of fetal abnormalities in rats (tarsal flexure of the hind paw at 2 mg/kg/day; equivalent to the human dose based on mg/m^2) and non-ossification of the odontoid and ventral tubercle of the first cervical vertebra at doses ≥0.1 mg/kg/day. Fulvestrant administered at 2 mg/kg/day caused fetal loss.

When administered to pregnant rabbits during the period of organogenesis, fulvestrant caused pregnancy loss at an intramuscular dose of 1 mg/kg/day (equivalent to the human dose based on mg/m^2). Further, at 0.25 mg/kg/day (30% the human dose based on mg/m^2), fulvestrant caused increases in placental weight and post-implantation loss in rabbits. Fulvestrant was associated with an increased incidence of fetal variations in rabbits (backwards displacement of the pelvic girdle, and 27 pre-sacral vertebrae at 0.25 mg/kg/day; 30% the human dose based on mg/m^2) when administered during the period of organogenesis.

8.2 Lactation

Risk Summary

There is no information regarding the presence of fulvestrant in human milk, nor of its effects on milk production or breastfed infant. Fulvestrant can be detected in rat milk [see Data]. Because of the potential for serious adverse reactions in breastfed infants from FASLODEX, advise a lactating woman not to breastfeed during treatment with FASLODEX and for one year after the final dose.

Data

Levels of fulvestrant were approximately 12-fold higher in milk than in plasma after exposure of lactating rats to a dose of 2 mg/kg. Drug exposure in rodent pups from fulvestrant-treated lactating dams was estimated as 10% of the administered dose. In a study in rats of fulvestrant at 10 mg/kg given twice or 15 mg/kg given once (less than the recommended human dose based on mg/m^2) during lactation, offspring survival was slightly reduced.

8.3 Females and Males of Reproductive Potential

Pregnancy Testing

Pregnancy testing is recommended for females of reproductive potential within seven days prior to initiating FASLODEX.

Contraception

Females

FASLODEX can cause fetal harm when administered to a pregnant woman [see Use in Specific Populations (8.1)]. Advise females of reproductive potential to use effective contraception during treatment and for one year after the last dose.

Infertility

Based on animal studies, FASLODEX may impair fertility in females and males of reproductive potential. The effects of fulvestrant on fertility were reversible in female rats [see Nonclinical Toxicology (13.1)].

8.4 Pediatric Use

Safety and effectiveness in pediatric patients have not been established. A multi-center, single-arm, open-label, study of fulvestrant was conducted in 30 girls with McCune-Albright Syndrome (MAS) associated with Progressive Precocious Puberty (PPP). The median age at informed consent was 6 years old (range: 1 to 8).

The first 10 patients initially received fulvestrant 2 mg/kg. Based on PK data from the first 6 patients, all 10 patients receiving 2 mg/kg were escalated to a dose of 4 mg/kg and all other patients received 4 mg/kg from study entry.

Baseline measurements for vaginal bleeding days, bone age, growth velocity, and Tanner staging for at least 6 months prior to study entry were provided retrospectively by the parent, guardian, or local consultant. All measurements during the study period were collected prospectively. Patients’ baseline characteristics included the following: a mean ± SD chronological age of 5.9 ± 1.8 years; a mean rate of bone age advancement (change in bone age in years divided by change in chronological age in years) of 2.0 ± 1.03; and a mean growth velocity z-score of 2.4 ± 3.26.

Twenty-nine of 30 patients completed the 12-month study period. The following results were observed: 35% (95% CI: 16%, 57%) of the 23 patients with baseline vaginal bleeding experienced a complete cessation of vaginal bleeding on-treatment (month 0 to 12); a reduction in the rate of bone age advancement during the 12-month study period compared to baseline (mean change=-0.9 [95% CI: -1.4, -0.4]); and a reduction in mean growth velocity Z-score on-treatment compared to baseline (mean change=-1.1 [95% CI: -2.7, 0.4]). There were no clinically meaningful changes in median Tanner stage (breast or pubic), mean uterine volume, or mean ovarian volume, or predicted adult height (PAH) on-treatment compared to baseline. The effect of FASLODEX on bone mineral density in children has not been studied and is not known.

Eight patients (27%) experienced adverse reactions that were considered possibly related to FASLODEX. These included injection site reactions (inflammation, pain, hematoma, pruritus, rash), abdominal pain, contusion, tachycardia, hot flash, extremity pain, and vomiting. Nine (30%) patients reported an SAE, none of which were considered related to FASLODEX. No patients discontinued study treatment due to an AE and no patients died.

Pharmacokinetics

The pharmacokinetics of fulvestrant was characterized using a population pharmacokinetic analysis with sparse samples per patient obtained from 30 female pediatric patients aged 1 to 8 years with PPP associated with MAS. Pharmacokinetic data from 294 postmenopausal women with breast cancer who received 125 or 250 mg monthly dosing regimen were also included in the analysis.

In these pediatric patients receiving 4 mg/kg monthly intramuscular dose of fulvestrant, the geometric mean (SD) CL/F was 444 (165) mL/min which was 32% lower than adults. The geometric mean (SD) steady state trough concentration (Cmin,ss) and AUCss was 4.19 (0.87) ng/mL and 3680 (1020) ng*hr/mL, respectively.

8.5 Geriatric Use

For FASLODEX 250 mg, when tumor response was considered by age, objective responses were seen in 22% and 24% of patients under 65 years of age and in 11% and 16% of patients 65 years of age and older, who were treated with FASLODEX in Study 0021 and Study 0020, respectively.

8.6 Hepatic Impairment

FASLODEX is metabolized primarily in the liver.

The pharmacokinetics of fulvestrant were evaluated after a single dose of 100 mg in subjects with mild and moderate hepatic impairment and normal hepatic function (n=7 subjects/group), using a shorter-acting intramuscular injection formulation. Subjects with mild hepatic impairment (Child-Pugh class A) had comparable mean AUC and clearance values to those with normal hepatic function. In subjects with moderate hepatic impairment (Child-Pugh class B), the average AUC of fulvestrant increased by 70% compared to patients with normal hepatic function. AUC was positively correlated with total bilirubin concentration (p=0.012). FASLODEX has not been studied in patients with severe hepatic impairment (Child-Pugh class C).

A dose of FASLODEX 250 mg is recommended in patients with moderate hepatic impairment (Child-Pugh class B) [see Dosage and Administration (2.2) and Warnings and Precautions (5.2)].

8.7 Renal Impairment

Negligible amounts of fulvestrant are eliminated in urine; therefore, a study in patients with renal impairment was not conducted. In the advanced breast cancer trials, fulvestrant concentrations in women with estimated creatinine clearance as low as 30 mL/min were similar to women with normal creatinine.

10 OVERDOSAGE

Human experience of overdose with FASLODEX is limited. There are isolated reports of overdose with FASLODEX in humans. No adverse reactions were seen in healthy male and female volunteers who received intravenous fulvestrant, which resulted in peak plasma concentrations at the end of the infusion, that were approximately 10 to 15 times those seen after intramuscular injection. The potential toxicity of fulvestrant at these or higher concentrations in cancer patients who may have additional comorbidities is unknown. There is no specific treatment in the event of fulvestrant overdose, and symptoms of overdose are not established. In the event of an overdose, healthcare practitioners should follow general supportive measures and should treat symptomatically.

11 DESCRIPTION

FASLODEX® (fulvestrant) injection for intramuscular administration is an estrogen receptor antagonist. The chemical name is 7-alpha-[9-(4,4,5,5,5-penta fluoropentylsulphinyl) nonyl]estra-1,3,5-(10)- triene-3,17-beta-diol. The molecular formula is C32H47F5O3S and its structural formula is:

Fulvestrant is a white powder with a molecular weight of 606.77. The solution for injection is a clear, colorless to yellow, viscous liquid.

Each injection contains as inactive ingredients: 10% w/v Alcohol, USP, 10% w/v Benzyl Alcohol, NF, and 15% w/v Benzyl Benzoate, USP, as co-solvents, and made up to 100% w/v with Castor Oil, USP as a co-solvent and release rate modifier.

12 CLINICAL PHARMACOLOGY

12.1 Mechanism of Action

Many breast cancers have estrogen receptors (ER) and the growth of these tumors can be stimulated by estrogen. Fulvestrant is an estrogen receptor antagonist that binds to the estrogen receptor in a competitive manner with affinity comparable to that of estradiol and downregulates the ER protein in human breast cancer cells.

In vitro studies demonstrated that fulvestrant is a reversible inhibitor of the growth of tamoxifen-resistant, as well as estrogen-sensitive human breast cancer (MCF-7) cell lines. In in vivo tumor studies, fulvestrant delayed the establishment of tumors from xenografts of human breast cancer MCF-7 cells in nude mice. Fulvestrant inhibited the growth of established MCF-7 xenografts and of tamoxifen-resistant breast tumor xenografts.

Fulvestrant showed no agonist-type effects in in vivo uterotrophic assays in immature or ovariectomized mice and rats. In in vivo studies in immature rats and ovariectomized monkeys, fulvestrant blocked the uterotrophic action of estradiol. In postmenopausal women, the absence of changes in plasma concentrations of FSH and LH in response to fulvestrant treatment (250 mg monthly) suggests no peripheral steroidal effects.

12.2 Pharmacodynamics

In a clinical study in postmenopausal women with primary breast cancer treated with single doses of FASLODEX 15-22 days prior to surgery, there was evidence of increasing down-regulation of ER with increasing dose. This was associated with a dose-related decrease in the expression of the progesterone receptor, an estrogen-regulated protein. These effects on the ER pathway were also associated with a decrease in Ki67 labeling index, a marker of cell proliferation.

12.3 Pharmacokinetics

Absorption:

The single dose and multiple dose PK parameters for the 500 mg dosing regimen with an additional dose (AD) at Day 15 are reported in Table 11. The additional dose of FASLODEX given two weeks after the initial dose allows for steady state concentrations to be reached within the first month of dosing.

Table 11: Summary of Fulvestrant Pharmacokinetic Parameters [gMean (CV%)] in Postmenopausal Advanced Breast Cancer Patients after Intramuscular Administration 500 mg + AD Dosing Regimen
 |  | Cmax (ng/mL) | Cmin (ng/mL) | AUC (ng.hr/mL)
500 mg + AD [Additional 500 mg dose given on Day 15] | Single dose | 25.1 (35.3) | 16.3 (25.9) | 11400 (33.4)
500 mg + AD [Additional 500 mg dose given on Day 15] | Multiple dose steady state [Month 3] | 28.0 (27.9) | 12.2 (21.7) | 13100 (23.4)

Distribution:

The apparent volume of distribution at steady state is approximately 3 to 5 L/kg. This suggests that distribution is largely extravascular. Fulvestrant is highly (99%) bound to plasma proteins; VLDL, LDL, and HDL lipoprotein fractions appear to be the major binding components. The role of sex hormone-binding globulin, if any, could not be determined.

Metabolism:

Biotransformation and disposition of fulvestrant in humans have been determined following intramuscular and intravenous administration of ^14C-labeled fulvestrant. Metabolism of fulvestrant appears to involve combinations of a number of possible biotransformation pathways analogous to those of endogenous steroids, including oxidation, aromatic hydroxylation, conjugation with glucuronic acid and/or sulphate at the 2, 3, and 17 positions of the steroid nucleus, and oxidation of the side chain sulphoxide. Identified metabolites are either less active or exhibit similar activity to fulvestrant in antiestrogen models.

Studies using human liver preparations and recombinant human enzymes indicate that cytochrome P-450 3A4 (CYP 3A4) is the only P-450 isoenzyme involved in the oxidation of fulvestrant; however, the relative contribution of P-450 and non-P-450 routes in vivo is unknown.

Excretion:

Fulvestrant was rapidly cleared by the hepatobiliary route with excretion primarily via the feces (approximately 90%). Renal elimination was negligible (less than 1%). After an intramuscular injection of 250 mg, the clearance (Mean ± SD) was 690 ± 226 mL/min with an apparent half-life about 40 days.

Special Populations:

Geriatric:

In patients with breast cancer, there was no difference in fulvestrant pharmacokinetic profile related to age (range 33 to 89 years).

Gender:

Following administration of a single intravenous dose, there were no pharmacokinetic differences between men and women or between premenopausal and postmenopausal women. Similarly, there were no differences between men and postmenopausal women after intramuscular administration.

Race:

In the advanced breast cancer treatment trials, the potential for pharmacokinetic differences due to race have been evaluated in 294 women including 87.4% Caucasian, 7.8% Black, and 4.4% Hispanic. No differences in fulvestrant plasma pharmacokinetics were observed among these groups. In a separate trial, pharmacokinetic data from postmenopausal ethnic Japanese women were similar to those obtained in non-Japanese patients.

Drug-Drug Interactions:

There are no known drug-drug interactions. Fulvestrant does not significantly inhibit any of the major CYP isoenzymes, including CYP 1A2, 2C9, 2C19, 2D6, and 3A4 in vitro, and studies of co-administration of fulvestrant with midazolam indicate that therapeutic doses of fulvestrant have no inhibitory effects on CYP 3A4 or alter blood levels of drug metabolized by that enzyme. Although fulvestrant is partly metabolized by CYP 3A4, a clinical study with rifampin, an inducer of CYP 3A4, showed no effect on the pharmacokinetics of fulvestrant. Also, results from a healthy volunteer study with ketoconazole, a potent inhibitor of CYP 3A4, indicated that ketoconazole had no effect on the pharmacokinetics of fulvestrant and dosage adjustment is not necessary in patients co-prescribed CYP 3A4 inhibitors or inducers [see Drug Interactions (7)]. Data from a clinical trial in patients with breast cancer showed that there was no clinically relevant drug interaction when fulvestrant is co-administered with palbociclib, abemaciclib, or ribociclib.

13 NONCLINICAL TOXICOLOGY

13.1 Carcinogenesis, Mutagenesis, Impairment of Fertility

Two-year carcinogenesis studies were conducted in rats and mice. Positive findings were observed in both species. Rats were treated at intramuscular doses of 15 mg/kg/30 days, 10 mg/rat/30 days, and 10 mg/rat/15 days.

These doses correspond to 0.9-, 1.5-, and 3-fold (in females) and 0.8-, 0.8-, and 2-fold (in males) the systemic exposure [AUC0-30 days] achieved in women receiving the recommended dose of 500 mg/month. An increased incidence of benign ovarian granulosa cell tumors and testicular Leydig cell tumors was evident, in females dosed at 10 mg/rat/15 days and males dosed at 15 mg/rat/30 days, respectively. Mice were treated at oral doses of 0, 20, 150, and 500 mg/kg/day. These doses correspond to 0-, 0.8-, 8.4-, and 18-fold (in females) and 0.8-, 7.1-, and 11.9-fold (in males), the systemic exposure (AUC0-30 days) achieved in women receiving the recommended dose of 500 mg/month. There was an increased incidence of sex cord stromal tumors (both benign and malignant) in the ovary of mice at doses of 150 and 500 mg/kg/day. Induction of such tumors is consistent with the pharmacology-related endocrine feedback alterations in gonadotropin levels caused by an antiestrogen.

Fulvestrant was not mutagenic or clastogenic in multiple in vitro tests with and without the addition of a mammalian liver metabolic activation factor (bacterial mutation assay in strains of Salmonella typhimurium and Escherichia coli, in vitro cytogenetics study in human lymphocytes, mammalian cell mutation assay in mouse lymphoma cells, and in vivo micronucleus test in rat).

In female rats, fulvestrant administered at doses ≥0.01 mg/kg/day (0.6% the human recommended dose based on body surface area [BSA in mg/m^2]), for 2 weeks prior to and for 1 week following mating, caused a reduction in fertility and embryonic survival. No adverse effects on female fertility and embryonic survival were evident in female animals dosed at 0.001 mg/kg/day (0.06% the human dose based on BSA in mg/m^2). Restoration of female fertility to values similar to controls was evident following a 29-day withdrawal period after dosing at 2 mg/kg/day (equivalent to the human dose based on BSA in mg/m^2). The effects of fulvestrant on the fertility of female rats appear to be consistent with its antiestrogenic activity. The potential effects of fulvestrant on the fertility of male animals were not studied, but in a 6-month toxicology study, male rats treated with intramuscular doses of 15 mg/kg/30 days, 10 mg/rat/30 days, or 10 mg/rat/15 days fulvestrant showed a loss of spermatozoa from the seminiferous tubules, seminiferous tubular atrophy, and degenerative changes in the epididymides. Changes in the testes and epididymides had not recovered 20 weeks after cessation of dosing. These fulvestrant doses correspond to 1.3-, 1.2-, and 3.5-fold the systemic exposure [AUC0-30 days] achieved in women receiving the recommended dose of 500 mg/month.

14 CLINICAL STUDIES

The efficacy of FASLODEX 500 mg versus FASLODEX 250 mg was compared in CONFIRM. The efficacy of FASLODEX 250 mg was compared to 1 mg anastrozole in Studies 0020 and 0021. The efficacy of FASLODEX 500 mg was compared to 1 mg anastrozole in FALCON. The efficacy of FASLODEX 500 mg in combination with palbociclib 125 mg was compared to FASLODEX 500 mg plus placebo in PALOMA-3. The efficacy of FASLODEX 500 mg in combination with abemaciclib 150 mg was compared to FASLODEX 500 mg plus placebo in MONARCH 2. The efficacy of FASLODEX 500 mg in combination with ribociclib 600 mg was compared to FASLODEX 500 mg plus placebo in MONALEESA-3.

Monotherapy

Comparison of FASLODEX 500 mg and FASLODEX 250 mg (CONFIRM)

A randomized, double-blind, controlled clinical trial (CONFIRM, NCT00099437) was completed in 736 postmenopausal women with advanced breast cancer who had disease recurrence on or after adjuvant endocrine therapy or progression following endocrine therapy for advanced disease. This trial compared the efficacy and safety of FASLODEX 500 mg (n=362) with FASLODEX 250 mg (n=374).

FASLODEX 500 mg was administered as two 5 mL injections each containing FASLODEX 250 mg/5 mL, one in each buttock, on Days 1, 15, 29, and every 28 (+/- 3) days thereafter. FASLODEX 250 mg was administered as two 5 mL injections (one containing FASLODEX 250 mg/5 mL injection plus one placebo injection), one in each buttock, on Days 1, 15 (2 placebo injections only), 29, and every 28 (+/- 3) days thereafter.

The median age of study participants was 61 years. All patients had ER+ advanced breast cancer. Approximately 30% of subjects had no measurable disease. Approximately 55% of patients had visceral disease.

Results of CONFIRM are summarized in Table 12. The efficacy of FASLODEX 500 mg was compared to that of FASLODEX 250 mg. Figure 6 shows a Kaplan-Meier plot of the Progression Free Survival (PFS) data after a minimum follow-up duration of 18 months demonstrating statistically significant superiority of FASLODEX 500 mg vs. FASLODEX 250 mg. In the initial Overall Survival (OS) analysis after a minimum follow-up duration of 18 months, there was no statistically significant difference in OS between the two treatment groups. After a minimum follow-up duration of 50 months, an updated OS analysis was performed. Figure 7 shows a Kaplan-Meier plot of the updated OS data.

Table 12: Efficacy Results in CONFIRM (Intent-To-Treat (ITT) Population)
Endpoint | FASLODEX 500 mg; (N=362) | FASLODEX 250 mg; (N=374)
PFS [PFS (Progression Free Survival)=the time between randomization and the earliest of progression or death from any cause. Minimum follow-up duration of 18 months.]; Median (months) | 6.5 | 5.4
Hazard Ratio [Hazard Ratio <1 favors FASLODEX 500 mg.] (95% CI [CI=Confidence Interval]) | 0.80 (0.68-0.94)
p-value | 0.006
OS [OS=Overall Survival] Updated Analysis [Minimum follow up duration of 50 months.]; (% patients who died) | 261 (72.1%) | 293 (78.3%)
Median OS (months) | 26.4 | 22.3
Hazard Ratio (95% CI) [Not statistically significant as no adjustments were made for multiplicity.] | 0.81 (0.69-0.96)
ORR [ORR (Objective Response Rate), as defined as number (%) of patients with complete response or partial response, was analyzed in the evaluable patients with measurable disease at baseline (fulvestrant 500 mg N=240; fulvestrant 250 mg N=261). Minimum follow-up duration of 18 months.] (95% CI) | 13.8% (9.7%, 18.8%); (33/240) | 14.6% (10.5%, 19.4%); (38/261)

Figure 6 Kaplan-Meier PFS: CONFIRM ITT Population

Figure 7 Kaplan-Meier OS (Minimum Follow-up Duration of 50 Months): CONFIRM ITT Population

Comparison of FASLODEX 500 mg and Anastrozole 1 mg (FALCON)

A randomized, double-blind, double-dummy, multi-center study (FALCON, NCT01602380) of FASLODEX 500 mg versus anastrozole 1 mg was conducted in postmenopausal women with ER-positive and/or PgR-positive, HER2-negative locally advanced or metastatic breast cancer who had not previously been treated with any hormonal therapy. A total of 462 patients were randomized 1:1 to receive administration of FASLODEX 500 mg as an intramuscular injection on Days 1, 15, 29, and every 28 (+/- 3) days thereafter or daily administration of 1 mg of anastrozole orally. This study compared the efficacy and safety of FASLODEX 500 mg and anastrozole 1 mg.

Randomization was stratified by disease setting (locally advanced or metastatic), use of prior chemotherapy for advanced disease, and presence or absence of measurable disease.

The major efficacy outcome measure of the study was investigator-assessed progression-free survival (PFS) evaluated according to RECIST v.1.1 (Response Evaluation Criteria in Solid Tumors). Key secondary efficacy outcome measures included overall survival (OS), objective response rate (ORR), and duration of response (DoR).

Patients enrolled in this study had a median age of 63 years (range 36-90). The majority of patients (87%) had metastatic disease at baseline. Fifty-five percent (55%) of patients had visceral metastasis at baseline. A total of 17% of patients had received one prior chemotherapy regimen for advanced disease; 84% of patients had measurable disease. Sites of metastases were as follows: musculoskeletal 59%, lymph nodes 50%, respiratory 40%, liver (including gall bladder) 18%.

The efficacy results of FALCON are presented in Table 13 and Figure 8.

Table 13: Efficacy Results in FALCON (Investigator Assessment, ITT Population)
 | FASLODEX; 500 mg; N=230 | Anastrozole; 1 mg; N=232
Progression-Free Survival
Number of PFS Events (%) | 143 (62.2%) | 166 (71.6%)
Median PFS (months) | 16.6 | 13.8
PFS Hazard Ratio (95% CI) | 0.797 (0.637 - 0.999)
p-value | 0.049
Overall Survival [Interim OS analysis with 61% of total number of events required for the final OS analysis.]
Number of OS Events | 67 (29.1%) | 75 (32.3%)
Median OS (months) | NR | NR
OS Hazard Ratio (95% CI) | 0.874 (0.629 – 1.216)
Objective Response for Patients with Measurable Disease | N=193 | N=196
Objective Response Rate (%, 95% CI) | 46.1% (38.9%, 53.4%) | 44.9% (37.8%, 52.1%)
Median DoR (months) | 20.0 | 13.2
NR: Not reached

Figure 8 Kaplan-Meier Plot of Progression-Free Survival (Investigator Assessment, ITT Population) ─ FALCON

Comparison of FASLODEX 250 mg and Anastrozole 1 mg in Combined Data (Studies 0020 and 0021)

Efficacy of FASLODEX was established by comparison to the selective aromatase inhibitor anastrozole in two randomized, controlled clinical trials (one conducted in North America, Study 0021, NCT00635713; the other predominantly in Europe, Study 0020) in postmenopausal women with locally advanced or metastatic breast cancer. All patients had progressed after previous therapy with an antiestrogen or progestin for breast cancer in the adjuvant or advanced disease setting.

The median age of study participants was 64 years. 81.6% of patients had ER+ and/or PgR+ tumors. Patients with ER-/PgR- or unknown tumors were required to have demonstrated a prior response to endocrine therapy. Sites of metastases occurred as follows: visceral only 18.2%; viscera – liver involvement 23.0%; lung involvement 28.1%; bone only 19.7%; soft tissue only 5.2%; skin and soft tissue 18.7%.

In both trials, eligible patients with measurable and/or evaluable disease were randomized to receive either FASLODEX 250 mg intramuscularly once a month (28 days + 3 days) or anastrozole 1 mg orally once a day. All patients were assessed monthly for the first three months and every three months thereafter. Study 0021 was a double-blind, randomized trial in 400 postmenopausal women. Study 0020 was an open-label, randomized trial conducted in 451 postmenopausal women. Patients on the FASLODEX arm of Study 0021 received two separate injections (2 x 2.5 mL), whereas FASLODEX patients received a single injection (1 x 5 mL) in Study 0020. In both trials, patients were initially randomized to a 125 mg per month dose as well, but interim analysis showed a very low response rate, and low dose groups were dropped.

Results of the trials, after a minimum follow-up duration of 14.6 months, are summarized in Table 14. The effectiveness of FASLODEX 250 mg was determined by comparing Objective Response Rate (ORR) and Time to Progression (TTP) results to anastrozole 1 mg, the active control. The two studies ruled out (by one-sided 97.7% confidence limit) inferiority of FASLODEX to anastrozole of 6.3% and 1.4% in terms of ORR. There was no statistically significant difference in overall survival (OS) between the two treatment groups after a follow-up duration of 28.2 months in Study 0021 and 24.4 months in Study 0020.

Table 14: Efficacy Results in Studies 0020 and 0021 (Objective Response Rate (ORR) and Time to Progression (TTP))
 | Study 0021 (Double-Blind) |  | Study 0020 (Open-Label)
Endpoint | FASLODEX 250 mg N=206 | Anastrozole 1 mg N=194 | FASLODEX 250 mg N=222 | Anastrozole 1 mg N=229
Objective Tumor Response Number (%) of subjects with CR [CR=Complete Response] + PR [PR=Partial Response] | 35 (17.0) | 33 (17.0) | 45 (20.3) | 34 (14.9)
% Difference in Tumor Response Rate (FAS [FAS=FASLODEX] -ANA [ANA=anastrozole]) 2-sided 95.4% CI [CI=Confidence Interval] | 0.0; (-6.3, 8.9) |  | 5.4; (-1.4, 14.8)
Time to Progression (TTP); Median TTP (days) | 165 | 103 | 166 | 156
Hazard Ratio [Hazard Ratio <1 favors FASLODEX]; 2-sided 95.4% CI | 0.9; (0.7, 1.1) |  | 1.0; (0.8, 1.2)
Stable Disease for ≥24 weeks (%) | 26.7 | 19.1 | 24.3 | 30.1
Overall Survival (OS)
Died n (%); Median Survival (days) | 152 (73.8%); 844 | 149 (76.8%); 913 | 167 (75.2%); 803 | 173 (75.5%); 736
Hazard Ratio; (2-sided 95% CI) | 0.98; (0.78, 1.24) |  | 0.97; (0.78, 1.21)

Combination Therapy

Patients with HR-positive, HER2-negative advanced or metastatic breast cancer who have had disease progression on or after prior adjuvant or metastatic endocrine therapy

FASLODEX 500 mg in Combination with Palbociclib 125 mg (PALOMA-3)

PALOMA-3 (NCT-1942135) was an international, randomized, double-blind, parallel group, multi-center study of FASLODEX plus palbociclib versus FASLODEX plus placebo conducted in women with HR-positive, HER2-negative advanced breast cancer, regardless of their menopausal status, whose disease progressed on or after prior endocrine therapy.

A total of 521 pre/postmenopausal women were randomized 2:1 to FASLODEX plus palbociclib or FASLODEX plus placebo and stratified by documented sensitivity to prior hormonal therapy, menopausal status at study entry (pre/peri versus postmenopausal), and presence of visceral metastases. Palbociclib was given orally at a dose of 125 mg daily for 21 consecutive days followed by 7 days off treatment. Fulvestrant 500 mg was administered as two 5 mL injections each containing fulvestrant 250 mg/5 mL, one in each buttock, on Days 1, 15, 29, and every 28 (+/- 3) days thereafter. Pre/perimenopausal women were enrolled in the study and received the LHRH agonist goserelin for at least 4 weeks prior to and for the duration of PALOMA-3.

Patients continued to receive assigned treatment until objective disease progression, symptomatic deterioration, unacceptable toxicity, death, or withdrawal of consent, whichever occurred first. The major efficacy outcome of the study was investigator-assessed PFS evaluated according to RECIST v.1.1.

Patients enrolled in this study had a median age of 57 years (range 29 to 88). The majority of patients on study were White (74%), all patients had an ECOG PS of 0 or 1, and 80% were postmenopausal. All patients had received prior systemic therapy and 75% of patients had received a previous chemotherapy regimen. Twenty-five percent of patients had received no prior therapy in the metastatic disease setting, 60% had visceral metastases, and 23% had bone only disease.

The results from the investigator-assessed PFS and final OS data from PALOMA-3 are summarized in Table 15. The relevant Kaplan-Meier plots are shown in Figures 9 and 10, respectively. Consistent PFS results were observed across patient subgroups of disease site, sensitivity to prior hormonal therapy, and menopausal status. After a median follow-up time of 45 months, the final OS results were not statistically significant.

Table 15: Efficacy Results in PALOMA-3 (Investigator Assessment, ITT Population)
 | FASLODEX plus Palbociclib | FASLODEX plus Placebo
Progression-Free Survival for ITT | N=347 | N=174
Number of PFS Events (%) | 145 (41.8%) | 114 (65.5%)
Median PFS (months) (95% CI) | 9.5 (9.2-11.0) | 4.6 (3.5-5.6)
Hazard Ratio (95% CI) and p-value | 0.461 (0.360-0.591); p <0.0001
Objective Response for Patients with Measurable Disease | N=267 | N=138
Objective response rate [Responses are based on confirmed responses.] (%, 95% CI) | 24.6 (19.6-30.2) | 10.9 (6.2-17.3)
Overall Survival for ITT population | N=347 | N=174
Number of OS events (%) | 201 (57.9) | 109 (62.6)
Median OS (months) (95% CI) | 34.9 (28.8, 40.0) | 28.0 (23.6, 34.6)
Hazard Ratio (95% CI) and p-value | 0.814 (0.644, 1.029), p=0.0857 [Not statistically significant at the pre-specified 2-sided alpha level of 0.047.] [2-sided p-value from the log-rank test stratified by the presence of visceral metastases and sensitivity to prior endocrine therapy per randomization.]
N=number of patients; PFS=progression-free survival; CI=confidence interval; ITT=Intent-to-Treat; OS=overall survival.

Figure 9 Kaplan-Meier Plot of Progression-Free Survival (Investigator Assessment, ITT Population) – PALOMA-3

Figure 10 Kaplan-Meier Plot of Overall Survival (ITT Population) ─ PALOMA-3

FASLODEX 500 mg in Combination with Abemaciclib 150 mg (MONARCH 2)

MONARCH 2 (NCT02107703) was a randomized, placebo-controlled, multi-center study conducted in women with HR-positive, HER2-negative metastatic breast cancer with disease progression following endocrine therapy treated with FASLODEX plus abemaciclib versus FASLODEX plus placebo. Randomization was stratified by disease site (visceral, bone only, or other) and by sensitivity to prior endocrine therapy (primary or secondary resistance). A total of 669 patients received intramuscular injection of FASLODEX 500 mg on Days 1 and 15 of cycle 1 and then on Day 1 of cycle 2 and beyond (28-day cycles), plus abemaciclib or placebo orally twice daily. Pre/perimenopausal women were enrolled in the study and received the gonadotropin-releasing hormone agonist goserelin for at least 4 weeks prior to and for the duration of MONARCH 2. Patients remained on continuous treatment until development of progressive disease or unmanageable toxicity.

Patient median age was 60 years (range, 32-91 years), and 37% of patients were older than 65. The majority were White (56%), and 99% of patients had an Eastern Cooperative Oncology Group (ECOG) performance status of 0 or 1. Twenty percent (20%) of patients had de novo metastatic disease, 27% had bone only disease, and 56% had visceral disease. Twenty-five percent (25%) of patients had primary endocrine therapy resistance. Seventeen percent (17%) of patients were pre- or perimenopausal.

The efficacy results from the MONARCH 2 study are summarized in Table 16, Figure 11, and Figure 12. PFS assessment based on a blinded independent radiologic review was consistent with the investigator assessment. Consistent results were observed across patient stratification subgroups of disease site and endocrine therapy resistance for PFS and OS.

Table 16: Efficacy Results in MONARCH 2 (Intent-to-Treat Population)
 | FASLODEX plus Abemaciclib | FASLODEX plus Placebo
Progression-Free Survival; (Investigator Assessment) | N=446 | N=223
Number of patients with an event (n, %) | 222 (49.8) | 157 (70.4)
Median (months, 95% CI) | 16.4 (14.4, 19.3) | 9.3 (7.4, 12.7)
Hazard ratio (95% CI) | 0.553 (0.449, 0.681)
p-value [Stratified by disease site (visceral metastases vs. bone-only metastases vs. other) and endocrine therapy resistance (primary resistance vs. secondary resistance)] | p<0.0001
Overall Survival [Data from a pre-specified interim analysis (77% of the number of events needed for the planned final analysis) with the p-value compared with the allocated alpha of 0.021.]
Number of deaths (n, %) | 211 (47.3) | 127 (57.0)
Median OS in months (95% CI) | 46.7 (39.2, 52.2) | 37.3 (34.4, 43.2)
Hazard ratio (95% CI)1 | 0.757 (0.606, 0.945)
p-value | p=0.0137
Objective Response for Patients with Measurable Disease | N=318 | N=164
Objective response rate [Complete response + partial response.] (n, %) | 153 (48.1) | 35 (21.3)
95% CI | 42.6, 53.6 | 15.1, 27.6
Abbreviations: CI=confidence interval, OS=overall survival.

Figure 11 Kaplan-Meier Curves of Progression-Free Survival: FASLODEX Plus Abemaciclib versus FASLODEX plus Placebo (MONARCH 2)

Figure 12 Kaplan-Meier Curves of Overall Survival: FASLODEX plus Abemaciclib versus FASLODEX plus Placebo (MONARCH 2)

Postmenopausal women with HR-positive, HER2-negative advanced or metastatic breast cancer for initial endocrine based therapy or after disease progression on endocrine therapy

FASLODEX 500 mg in Combination with Ribociclib 600 mg (MONALEESA-3)

MONALEESA-3 (NCT 02422615) was a randomized double-blind, placebo-controlled study of FASLODEX plus ribociclib versus FASLODEX plus placebo conducted in postmenopausal women with hormone receptor positive, HER2-negative, advanced breast cancer who have received no or only one line of prior endocrine treatment.

A total of 726 patients were randomized in a 2:1 ratio to receive FASLODEX plus ribociclib or FASLODEX plus placebo and stratified according to the presence of liver and/or lung metastases and prior endocrine therapy for advanced or metastatic disease. Fulvestrant 500 mg was administered intramuscularly on Days 1, 15, 29, and once monthly thereafter, with either ribociclib 600 mg or placebo given orally once daily for 21 consecutive days followed by 7 days off until disease progression or unacceptable toxicity. The major efficacy outcome measure for the study was investigator-assessed progression-free survival (PFS) using Response Evaluation Criteria in Solid Tumors (RECIST) v1.1.

Patients enrolled in this study had a median age of 63 years (range 31 to 89). Of the patients enrolled, 47% were 65 years and older, including 14% age 75 years and older. The patients enrolled were primarily Caucasian (85%), Asian (9%), and Black (0.7%). Nearly all patients (99.7%) had an ECOG performance status of 0 or 1. First- and second-line patients were enrolled in this study (of which 19% had de novo metastatic disease). Forty-three percent (43%) of patients had received chemotherapy in the adjuvant vs. 13% in the neoadjuvant setting and 59% had received endocrine therapy in the adjuvant vs. 1% in the neoadjuvant setting prior to study entry. Twenty-one percent (21%) of patients had bone-only disease and 61% had visceral disease. Demographics and baseline disease characteristics were balanced and comparable between study arms.

The efficacy results from MONALEESA-3 are summarized in Table 17, Figure 13, and Figure 14. Consistent results were observed in stratification factor subgroups of disease site and prior endocrine treatment for advanced disease.

Table 17: Efficacy Results – MONALEESA-3 (Investigator Assessment, Intent-to-Treat Population)
 | FASLODEX plus Ribociclib | FASLODEX plus Placebo
Progression-free survival [Investigator Assessment] | N=484 | N=242
Events (n, %) | 210 (43.4%) | 151 (62.4%)
Median (months, 95% CI) | 20.5 (18.5, 23.5) | 12.8 (10.9, 16.3)
Hazard Ratio (95% CI) | 0.593 (0.480 to 0.732)
p-value [p-value is obtained from the one-sided log-rank] | <0.0001
Overall Survival | N=484 | N=242
Events (n, %) | 167 (34.5%) | 108 (44.6%)
Median (months, 95% CI) | NR (42.5, NR) | 40.0 (37.0, NR)
Hazard Ratio (95% CI) | 0.724 (0.568, 0.924)
p-value | 0.00455
Overall Response Rate [Based on confirmed responses] | N=379 | N=181
Patients with measurable disease (95% CI) | 40.9 (35.9, 45.8) | 28.7 (22.1, 35.3)
Abbreviation: NR, not reached

Figure 13 Kaplan-Meier Progression Free Survival Curves – MONALEESA-3 (Intent-To-Treat Population, Investigator assessment)

Figure 14 Kaplan-Meier plot of Overall Survival – MONALEESA-3 (Intent -to-Treat Population)

16 HOW SUPPLIED/STORAGE AND HANDLING

FASLODEX is supplied as two 5 mL clear neutral glass (Type 1) barrels, each containing 250 mg/5 mL of FASLODEX solution for intramuscular injection and fitted with a tamper evident closure.

NDC 0310–0720–10

The single-dose prefilled syringes are presented in a tray with polystyrene plunger rod and safety needles (SafetyGlide™) for connection to the barrel.

Discard each syringe after use. If a patient dose requires only one syringe, unused syringe should be stored as directed below.

Storage:

REFRIGERATE, 2°-8°C (36°-46°F). TO PROTECT FROM LIGHT, STORE IN THE ORIGINAL CARTON UNTIL TIME OF USE.

17 PATIENT COUNSELING INFORMATION

Advise the patient to read the FDA-approved patient labeling (Patient Information).

Monotherapy

Risk of Bleeding:

- Because FASLODEX is administered intramuscularly, it should be used with caution in patients with bleeding disorders, decreased platelet count, or in patients receiving anticoagulants (for example, warfarin) [see Warnings and Precautions (5.1)].

Embryo-Fetal Toxicity:

- Advise females of reproductive potential of the potential risk to a fetus and to use effective contraception during treatment with FASLODEX and for one year after the last dose. Advise females to inform their healthcare provider of a known or suspected pregnancy [see Warnings and Precautions (5.4) and Use in Specific Populations (8.1), (8.3)].

Lactation:

- Advise women not to breastfeed during treatment with FASLODEX and for one year after the last dose [see Use in Specific Populations (8.2)].

Combination Therapy

When FASLODEX is used in combination with palbociclib, abemaciclib, or ribociclib, refer to the respective Full Prescribing Information for Patient Counseling Information.

Distributed by:

AstraZeneca Pharmaceuticals LP

Wilmington, DE 19850

FASLODEX is a registered trademark of the AstraZeneca group of companies

©AstraZeneca 2020

PATIENT INFORMATION

FASLODEX® (faz-lo-dex)

(fulvestrant)

injection

What is FASLODEX?

FASLODEX is a prescription medicine used to treat advanced breast cancer or breast cancer that has spread to other parts of the body (metastatic).

FASLODEX may be used alone, if you have gone through menopause, and your advanced breast cancer is:

- hormone receptor (HR)-positive and human epidermal growth factor receptor 2 (HER2)-negative and has not been previously treated with endocrine therapy
  or
- HR-positive and has progressed after endocrine therapy.

FASLODEX may be used in combination with ribociclib, if you have gone through menopause, and your advanced or metastatic breast cancer is HR-positive and HER2-negative, and has not been previously treated with endocrine therapy or has progressed after endocrine therapy.

FASLODEX may be used in combination with palbociclib or abemaciclib if your advanced or metastatic breast cancer is HR-positive and HER2-negative, and has progressed after endocrine therapy.

When FASLODEX is used in combination with palbociclib, abemaciclib, or ribociclib, also read the Patient Information for the prescribed product.

It is not known if FASLODEX is safe and effective in children.

It is not known if FASLODEX is safe and effective in people with severe liver problems.

Who should not receive FASLODEX?

Do not receive FASLODEX if you have had an allergic reaction to fulvestrant or any of the ingredients in FASLODEX. See the end of this leaflet for a list of the ingredients in FASLODEX.

Symptoms of an allergic reaction to FASLODEX may include:

- itching or hives
- swelling of your face, lips, tongue, or throat
- trouble breathing

What should I tell my healthcare provider before receiving FASLODEX?

Before receiving FASLODEX, tell your healthcare provider about all of your medical conditions, including if you:

- have a low level of platelets in your blood or bleed easily.
- have liver problems.
- are pregnant or plan to become pregnant. FASLODEX can harm your unborn baby.
  Females who are able to become pregnant:
  - Your healthcare provider may perform a pregnancy test within 7 days before you start FASLODEX.
  - You should use effective birth control during treatment with FASLODEX and for one year after the last dose of FASLODEX.
  - Tell your healthcare provider right away if you become pregnant or think you are pregnant during treatment with FASLODEX.
- are breastfeeding or plan to breastfeed. It is not known if FASLODEX passes into your breast milk. Do not breastfeed during your treatment with FASLODEX and for one year after the final dose of FASLODEX. Talk to your healthcare provider about the best way to feed your baby during this time.

Tell your healthcare provider about all the medicines you take, including prescription and over-the-counter medicines, vitamins, and herbal supplements. FASLODEX may affect the way other medicines work, and other medicines may affect how FASLODEX works.

Especially tell your healthcare provider if you take a blood thinner medicine.

How will I receive FASLODEX?

- Your healthcare provider will give you FASLODEX by injection into the muscle of each buttock.
- Your healthcare provider may change your dose of FASLODEX if needed.

What are the possible side effects of FASLODEX?

FASLODEX may cause serious side effects, including:

- Injection site related nerve damage. Call your healthcare provider if you develop any of the following symptoms in your legs following a FASLODEX injection:
  - numbness
  - tingling
  - weakness

The most common side effects of FASLODEX include:

- injection site pain
- nausea
- muscle, joint, and bone pain
- headache
- back pain
- tiredness
- pain in arms, hands, legs, or feet
- hot flashes
- vomiting

- loss of appetite
- weakness
- cough
- shortness of breath
- constipation
- increased liver enzymes
- diarrhea

FASLODEX may cause fertility problems in males and females. Talk to your healthcare provider if you plan to become pregnant.

Tell your healthcare provider if you have any side effect that bothers you or that does not go away.

These are not all of the possible side effects with FASLODEX. For more information, ask your healthcare provider or pharmacist.

Call your healthcare provider for medical advice about side effects. You may report side effects to FDA at 1-800-FDA-1088.

General information about the safe and effective use of FASLODEX

Medicines are sometimes prescribed for purposes other than those listed in a Patient Information leaflet. If you would like more information, talk with your healthcare provider. You can ask your pharmacist or healthcare provider for information about FASLODEX that is written for health professionals.

What are the ingredients in FASLODEX?

Active ingredient: fulvestrant.

Inactive ingredients: alcohol, benzyl alcohol, benzyl benzoate, and castor oil.

SafetyGlide™ is a trademark of Becton Dickinson and Company.

FASLODEX is a trademark of the AstraZeneca group of companies.

© AstraZeneca 2020

Distributed by:

AstraZeneca Pharmaceuticals LP

Wilmington, DE 19850

Manufactured for:

AstraZeneca UK Limited

Macclesfield, Cheshire, England

By: Vetter Pharma-Fertigung GMBH & Co. KG

Ravensburg, Germany

For more information, go to www.FASLODEX.com or call 1-800-236-9933.

This Patient Information has been approved by the U.S. Food and Drug Administration Revised: 8/2020

Package/Label Display Panel – 250 mg/5 mL (50 mg/mL)

FASLODEX®

fulvestrant injection

250 mg/5 mL (50 mg/mL)

For Intramuscular Use Only

AstraZeneca

NDC 0310-0720-10

This carton contains a total of 500 mg fulvestrant in TWO single-dose prefilled syringes each containing 250 mg/5 mL, and two Safety Glide™ shielding intramuscular injection needles.

Discard each syringe after use.

Both single-dose prefilled syringes must be administered to receive the 500 mg dose.

REFRIGERATE, 2-8°C (36-46°F). TO PROTECT FROM LIGHT, STORE IN THE ORIGINAL CARTON UNTIL TIME OF USE.

Rx only

Contains 2 single-dose prefilled syringes.